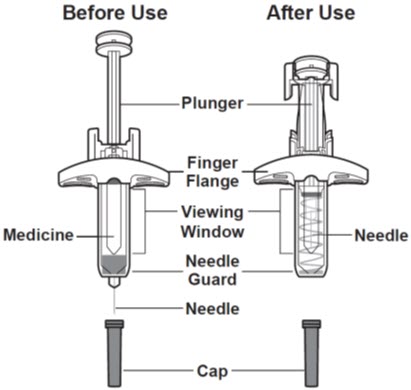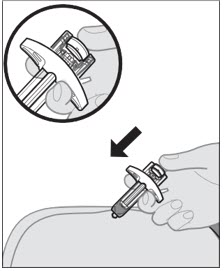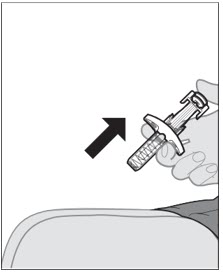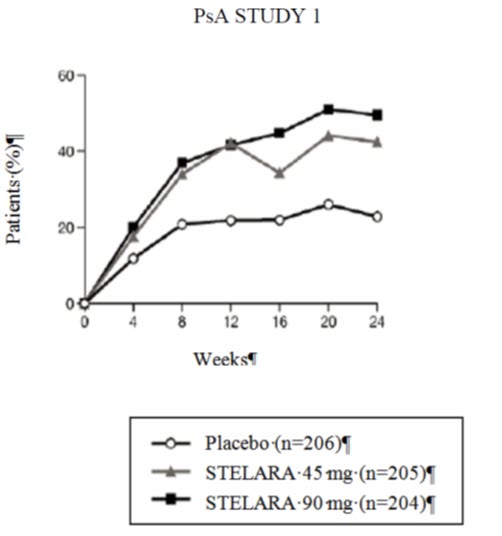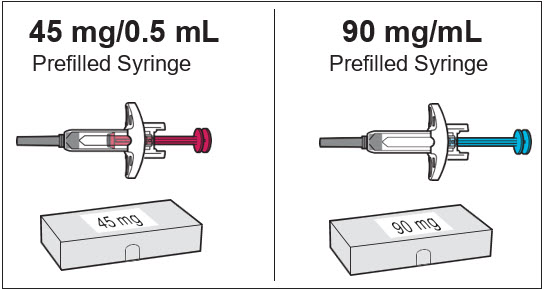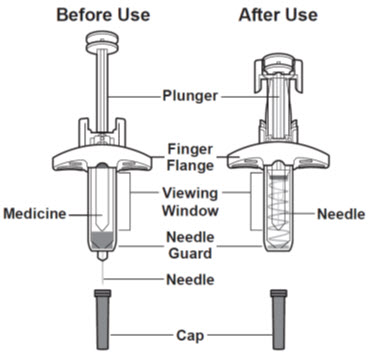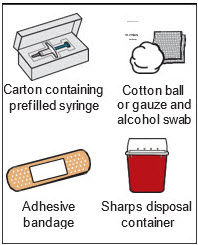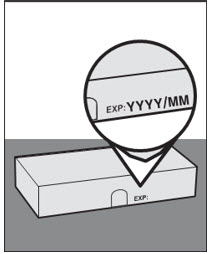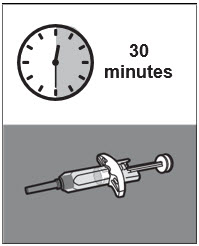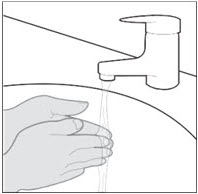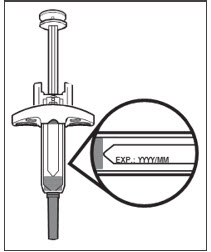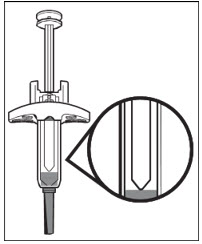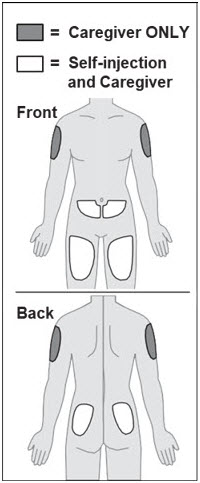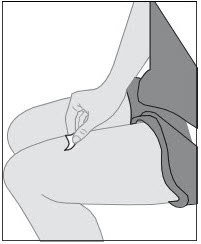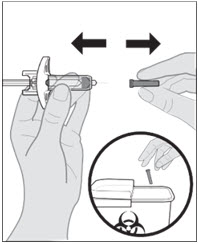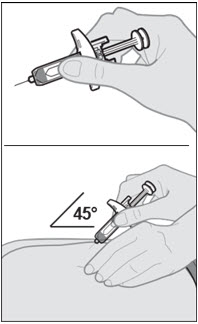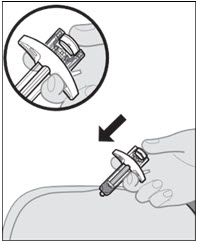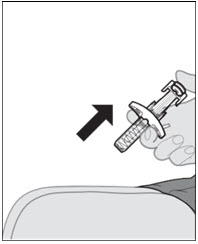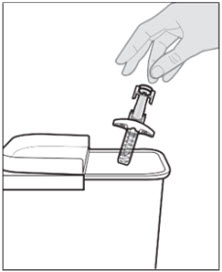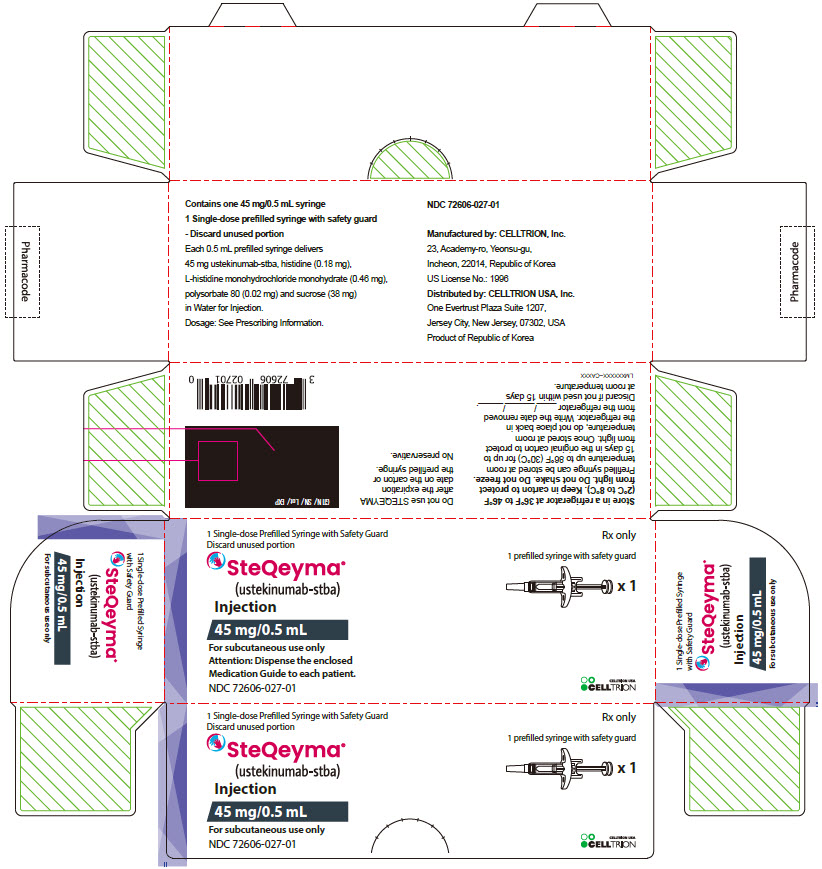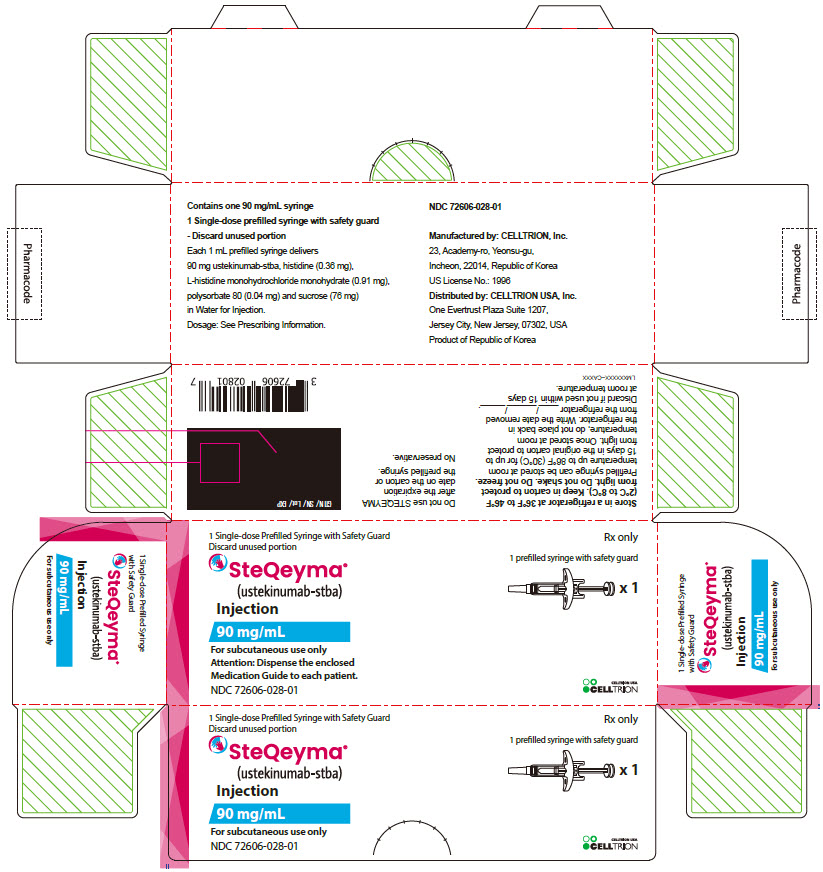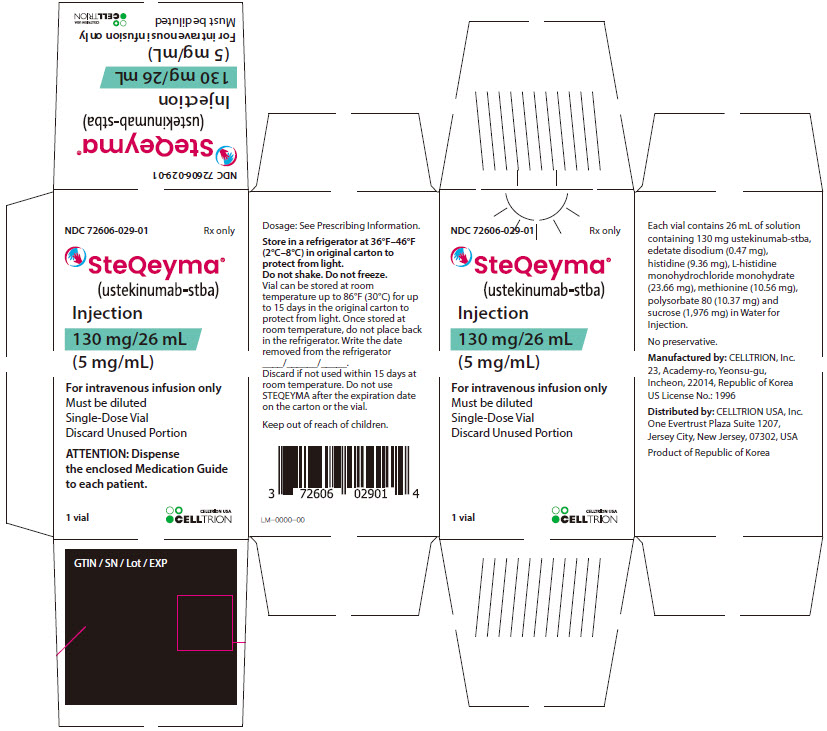 DRUG LABEL: STEQEYMA
NDC: 72606-027 | Form: INJECTION, SOLUTION
Manufacturer: CELLTRION USA Inc.
Category: prescription | Type: HUMAN PRESCRIPTION DRUG LABEL
Date: 20250421

ACTIVE INGREDIENTS: ustekinumab 45 mg/0.5 mL
INACTIVE INGREDIENTS: HISTIDINE 0.18 mg/0.5 mL; HISTIDINE MONOHYDROCHLORIDE MONOHYDRATE 0.46 mg/0.5 mL; Sucrose 38 mg/0.5 mL; Polysorbate 80 0.02 mg/0.5 mL; Water

HIGHLIGHTS OF PRESCRIBING INFORMATION

These highlights do not include all the information needed to use STEQEYMA safely and effectively. See full prescribing information for STEQEYMA.
STEQEYMA (ustekinumab-stba) injection, for subcutaneous or intravenous use
Initial U.S. Approval: 2024
STEQEYMA (ustekinumab-stba) is biosimilar [Biosimilar means that the biological product is approved based on data demonstrating that it is highly similar to an FDA-approved biological product, known as a reference product, and that there are no clinically meaningful differences between the biosimilar product and the reference product. Biosimilarity of STEQEYMA has been demonstrated for the condition(s) of use (e.g. indication(s), dosing regimen(s)), strength(s), dosage form(s), and route(s) of administration described in its Full Prescribing Information.] to STELARA® (ustekinumab)

1. INDICATIONS AND USAGE

STEQEYMA is a human interleukin-12 and -23 antagonist indicated for the treatment of:

Adult patients with:

- moderate to severe plaque psoriasis (PsO) who are candidates for phototherapy or systemic therapy. (1.1)
- active psoriatic arthritis (PsA). (1.2)
- moderately to severely active Crohn's disease (CD). (1.3)
- moderately to severely active ulcerative colitis. (1.4)

Pediatric patients 6 years and older with:

- moderate to severe plaque psoriasis, who are candidates for phototherapy or systemic therapy. (1.1)
- active psoriatic arthritis (PsA). (1.2)

2. DOSAGE AND ADMINISTRATION

Psoriasis Adult Subcutaneous Recommended Dosage (2.1):

Weight Range (kilograms) | Recommended Dosage
less than or equal to 100 kg | 45 mg administered subcutaneously initially and 4 weeks later, followed by 45 mg administered subcutaneously every 12 weeks
greater than 100 kg | 90 mg administered subcutaneously initially and 4 weeks later, followed by 90 mg administered subcutaneously every 12 weeks

Psoriasis Pediatric Patients (6 to 17 years old) Subcutaneous Recommended Dosage (2.1): Weight-based dosing is recommended at the initial dose, 4 weeks later, then every 12 weeks thereafter.

Weight Range (kilograms) | Dose
60 kg to 100 kg | 45 mg
greater than 100 kg | 90 mg

Psoriatic Arthritis Adult Subcutaneous Recommended Dosage (2.2):

- The recommended dosage is 45 mg administered subcutaneously initially and 4 weeks later, followed by 45 mg administered subcutaneously every 12 weeks.
- For patients with co-existent moderate-to-severe plaque psoriasis weighing greater than 100 kg, the recommended dosage is 90 mg administered subcutaneously initially and 4 weeks later, followed by 90 mg administered subcutaneously every 12 weeks.

Psoriatic Arthritis Pediatric (6 to 17 years old) Subcutaneous Recommended Dosage (2.2): Weight-based dosing is recommended at the initial dose, 4 weeks later, then every 12 weeks thereafter.

Weight Range (kilograms) | Dose
60 kg or more | 45 mg
greater than 100 kg with co-existent moderate-to-severe plaque psoriasis | 90 mg

Crohn's Disease and Ulcerative Colitis Initial Adult Intravenous Recommended Dosage (2.3): A single intravenous infusion using weight- based dosing:

Weight Range (kilograms) | Dose
up to 55 kg | 260 mg (2 vials)
greater than 55 kg to 85 kg | 390 mg (3 vials)
greater than 85 kg | 520 mg (4 vials)

Crohn's Disease and Ulcerative Colitis Maintenance Adult Subcutaneous Recommended Dosage (2.3): A subcutaneous 90 mg dose 8 weeks after the initial intravenous dose, then every 8 weeks thereafter.

3. DOSAGE FORMS AND STRENGTHS

Subcutaneous Injection (3)

- Injection: 45 mg/0.5 mL or 90 mg/mL solution in a single-dose prefilled syringe

Intravenous Infusion (3)

- Injection: 130 mg/26 mL (5 mg/mL) solution in a single-dose vial (3)

4. CONTRAINDICATIONS

Clinically significant hypersensitivity to ustekinumab products or to any of the excipients in STEQEYMA. (4)

5. WARNINGS AND PRECAUTIONS

- Infections: Serious infections have occurred. Avoid starting STEQEYMA during any clinically important active infection. If a serious infection or clinically significant infection develops, discontinue STEQEYMA until the infection resolves. (5.1)
- Theoretical Risk for Particular Infections: Serious infections from mycobacteria, salmonella, and Bacillus Calmette-Guerin (BCG) vaccinations have been reported in patients genetically deficient in IL-12/IL-23. Consider diagnostic tests for these infections as dictated by clinical circumstances. (5.2)
- Tuberculosis (TB): Evaluate patients for TB prior to initiating treatment with STEQEYMA. Initiate treatment of latent TB before administering STEQEYMA. (5.3)
- Malignancies: Ustekinumab products may increase risk of malignancy. The safety of ustekinumab products in patients with a history of or a known malignancy has not been evaluated. (5.4)
- Hypersensitivity Reactions: If an anaphylactic or other clinically significant hypersensitivity reaction occurs, institute appropriate therapy and discontinue STEQEYMA. (5.5)
- Posterior Reversible Encephalopathy Syndrome (PRES): If PRES is suspected, treat promptly, and discontinue STEQEYMA. (5.6)
- Immunizations: Avoid use of live vaccines in patients during treatment with STEQEYMA. (5.7)
- Noninfectious Pneumonia: Cases of interstitial pneumonia, eosinophilic pneumonia, and cryptogenic organizing pneumonia have been reported during post-approval use of ustekinumab products. If diagnosis is confirmed, discontinue STEQEYMA and institute appropriate treatment. (5.8)

6. ADVERSE REACTIONS

Most common adverse reactions are:

- Psoriasis (≥3%): nasopharyngitis, upper respiratory tract infection, headache, and fatigue. (6.1)
- Crohn's Disease, induction (≥3%): vomiting. (6.1)
- Crohn's Disease, maintenance (≥3%): nasopharyngitis, injection site erythema, vulvovaginal candidiasis/mycotic infection, bronchitis, pruritus, urinary tract infection, and sinusitis. (6.1)
- Ulcerative colitis, induction (≥3%): nasopharyngitis (6.1)
- Ulcerative colitis, maintenance (≥3%): nasopharyngitis, headache, abdominal pain, influenza, fever, diarrhea, sinusitis, fatigue, and nausea (6.1)

To report SUSPECTED ADVERSE REACTIONS, contact CELLTRION USA, Inc. at 1-800-560-9414 or FDA at 1-800-FDA-1088 or www.fda.gov/medwatch.

FULL PRESCRIBING INFORMATION

1. INDICATIONS AND USAGE

1.1. Plaque Psoriasis (PsO)

STEQEYMA is indicated for the treatment of adults and pediatric patients 6 years of age and older with moderate to severe plaque psoriasis who are candidates for phototherapy or systemic therapy.

1.2. Psoriatic Arthritis (PsA)

STEQEYMA is indicated for the treatment of adults and pediatric patients 6 years of age and older with active psoriatic arthritis.

1.3. Crohn's Disease (CD)

STEQEYMA is indicated for the treatment of adult patients with moderately to severely active Crohn's disease.

1.4. Ulcerative Colitis

STEQEYMA is indicated for the treatment of adult patients with moderately to severely active ulcerative colitis.

2. DOSAGE AND ADMINISTRATION

2.1. Recommended Dosage in Plaque Psoriasis

Subcutaneous Adult Dosage Regimen

- For patients weighing 100 kg or less, the recommended dosage is 45 mg initially and 4 weeks later, followed by 45 mg every 12 weeks.
- For patients weighing more than 100 kg, the recommended dosage is 90 mg initially and 4 weeks later, followed by 90 mg every 12 weeks.

In subjects weighing more than 100 kg, 45 mg was also shown to be efficacious. However, 90 mg resulted in greater efficacy in these subjects [see Clinical Studies (14)].

Subcutaneous Pediatric Dosage Regimen

Administer STEQEYMA subcutaneously at Weeks 0 and 4, then every 12 weeks thereafter.

The recommended dose of STEQEYMA for pediatric patients (6-17 years old) with plaque psoriasis based on body weight is shown below (Table 1).

Table 1: Recommended Dose of STEQEYMA for Subcutaneous Injection in Pediatric Patients (6-17 years old) with Plaque Psoriasis
Body Weight of Patient at the Time of Dosing | Recommended Dose
60 kg to 100 kg | 45 mg
more than 100 kg | 90 mg

There is no dosage form for STEQEYMA that allows weight-based dosing for pediatric patients below 60 kg.

2.2. Recommended Dosage in Psoriatic Arthritis

Subcutaneous Adult Dosage Regimen

- The recommended dosage is 45 mg initially and 4 weeks later, followed by 45 mg every 12 weeks.
- For patients with co-existent moderate-to-severe plaque psoriasis weighing more than 100 kg, the recommended dosage is 90 mg initially and 4 weeks later, followed by 90 mg every 12 weeks.

Subcutaneous Pediatric Dosage Regimen

Administer STEQEYMA subcutaneously at Weeks 0 and 4, then every 12 weeks thereafter.

The recommended dose of STEQEYMA for pediatric patients (6 to 17 years old) with psoriatic arthritis, based on body weight, is shown below (Table 2).

Table 2: Recommended Dose of STEQEYMA for Subcutaneous Injection in Pediatric Patients (6 to 17 years old) with Psoriatic Arthritis
Body Weight of Patient at the Time of Dosing | Recommended Dose
60 kg or more | 45 mg
greater than 100 kg with co-existent moderate-to-severe plaque psoriasis | 90 mg

There is no dosage form for STEQEYMA that allows weight-based dosing for pediatric patients below 60 kg.

2.3. Recommended Dosage in Crohn's Disease and Ulcerative Colitis

Intravenous Induction Adult Dosage Regimen

A single intravenous infusion dose of STEQEYMA using the weight-based dosage regimen specified in Table 3 [see Instructions for dilution of STEQEYMA 130 mg vial for intravenous infusion (2.6)].

Table 3: Initial Intravenous Dosage of STEQEYMA
Body Weight of Patient at the time of dosing | Dose | Number of 130 mg/26 mL (5 mg/mL) STEQEYMA vials
55 kg or less | 260 mg | 2
more than 55 kg to 85 kg | 390 mg | 3
more than 85 kg | 520 mg | 4

Subcutaneous Maintenance Adult Dosage Regimen

The recommended maintenance dosage is a subcutaneous 90 mg dose administered 8 weeks after the initial intravenous dose, then every 8 weeks thereafter.

2.4. General Considerations for Administration

- STEQEYMA is intended for use under the guidance and supervision of a healthcare provider. STEQEYMA should only be administered to patients who will be closely monitored and have regular follow-up visits with a healthcare provider. The appropriate dose should be determined by a healthcare provider using the patient's current weight at the time of dosing. In pediatric patients, it is recommended that STEQEYMA be administered by a healthcare provider. If a healthcare provider determines that it is appropriate, a patient may self-inject or a caregiver may inject STEQEYMA after proper training in subcutaneous injection technique. Instruct patients to follow the directions provided in the Medication Guide [see Medication Guide].
- It is recommended that each injection be administered at a different anatomic location (such as upper arms, gluteal regions, thighs, or any quadrant of abdomen) than the previous injection, and not into areas where the skin is tender, bruised, erythematous, or indurated.
- Parenteral drug products should be inspected visually for particulate matter and discoloration prior to administration, whenever solution and container permit. Prior to administration, visually inspect STEQEYMA for particulate matter and discoloration. STEQEYMA is a colorless to pale yellow solution and may contain a few small translucent or white particles. Do not use STEQEYMA if it is discolored or cloudy, or if other particulate matter is present. STEQEYMA does not contain preservatives; therefore, discard any unused product remaining in the vial and/or syringe.

2.5. Instructions for Administration of STEQEYMA Prefilled Syringes Equipped with Needle Safety Guard

Refer to the diagram below for the provided instructions.

- Remove the needle cap when you are ready to inject STEQEYMA by holding the body of the prefilled syringe in one hand between the thumb and index fingers. Do not hold the plunger while removing the cap. Do not use the prefilled syringe if it has been dropped without the needle cover in place.
- Inject STEQEYMA subcutaneously as recommended [see Dosage and Administration (2.1, 2.2, 2.3)].
- Inject all of the liquid by using your thumb to push the plunger all the way down. If the plunger is not fully pressed, the needle guard will not extend to cover the needle when it is removed.
- After the prefilled syringe is empty, slowly lift your thumb from the plunger rod until the needle is completely covered by the needle guard, as shown by the illustration below:
- Used syringes should be placed in a puncture-resistant container.

2.6. Preparation and Administration of STEQEYMA 130 mg/26 mL (5 mg/mL) Vial for Intravenous Infusion (Crohn's Disease and Ulcerative Colitis)

STEQEYMA solution for intravenous infusion must be diluted, prepared, and infused by a healthcare professional using aseptic technique.

1. Calculate the dose and the number of STEQEYMA vials needed based on patient weight (Table 3). Each 26 mL vial of STEQEYMA contains 130 mg of ustekinumab-stba.
2. Withdraw, and then discard a volume of the 0.9% Sodium Chloride Injection, USP from the 250 mL infusion bag equal to the volume of STEQEYMA to be added (discard 26 mL sodium chloride for each vial of STEQEYMA needed, for 2 vials- discard 52 mL, for 3 vials- discard 78 mL, 4 vials- discard 104 mL). Alternatively, a 250 mL infusion bag containing 0.45% Sodium Chloride Injection, USP may be used.
3. Withdraw 26 mL of STEQEYMA from each vial needed and add it to the 250 mL infusion bag. The final volume in the infusion bag should be 250 mL. Gently mix.
4. Parenteral drug products should be inspected visually for particulate matter and discoloration prior to administration, whenever solution and container permit. Do not use if visibly opaque particles, discoloration or foreign particles are observed.
5. Infuse the diluted solution over a period of at least one hour. Once diluted, the infusion should be completely administered within four hours of the dilution in the infusion bag.
6. Use only an infusion set with an in-line, sterile, non-pyrogenic, low protein-binding filter (pore size 0.2 micrometer).
7. Do not infuse STEQEYMA concomitantly in the same intravenous line with other agents.
8. STEQEYMA does not contain preservatives. Each vial is for one-time use in only one patient. Discard any remaining solution. Dispose any unused medicinal product in accordance with local requirements.

Storage

If necessary, the diluted infusion solution may be kept at room temperature up to 30°C (86°F) for up to 3 hours. Storage time at room temperature begins once the diluted solution has been prepared. The infusion should be completed within 4 hours after the dilution in the infusion bag (cumulative time after preparation including the storage and the infusion period). Do not freeze. Discard any unused portion of the infusion solution.

3. DOSAGE FORMS AND STRENGTHS

STEQEYMA (ustekinumab-stba) is a colorless to pale yellow solution and may contain a few small translucent or white particles.

Subcutaneous Injection

- Injection: 45 mg/0.5 mL or 90 mg/mL solution in a single-dose prefilled syringe

Intravenous Infusion

- Injection: 130 mg/26 mL (5 mg/mL) solution in a single-dose vial

4. CONTRAINDICATIONS

STEQEYMA is contraindicated in patients with clinically significant hypersensitivity to ustekinumab products or to any of the excipients in STEQEYMA [see Warnings and Precautions (5.5)].

5. WARNINGS AND PRECAUTIONS

5.1. Infections

Ustekinumab products may increase the risk of infections and reactivation of latent infections. Serious bacterial, mycobacterial, fungal, and viral infections were observed in patients receiving ustekinumab products [see Adverse Reactions (6.1, 6.3)].

Serious infections requiring hospitalization, or otherwise clinically significant infections, reported in clinical trials included the following:

- Plaque Psoriasis: diverticulitis, cellulitis, pneumonia, appendicitis, cholecystitis, sepsis, osteomyelitis, viral infections, gastroenteritis, and urinary tract infections.
- Psoriatic arthritis: cholecystitis.
- Crohn's disease: anal abscess, gastroenteritis, ophthalmic herpes zoster, pneumonia, and listeria meningitis.
- Ulcerative colitis: gastroenteritis, ophthalmic herpes zoster, pneumonia, and listeriosis.

Avoid initiating treatment with STEQEYMA in patients with any clinically important active infection until the infection resolves or is adequately treated. Consider the risks and benefits of treatment prior to initiating use of STEQEYMA in patients with a chronic infection or a history of recurrent infection.

Instruct patients to seek medical advice if signs or symptoms suggestive of an infection occur while on treatment with STEQEYMA and discontinue STEQEYMA for serious or clinically significant infections until the infection resolves or is adequately treated.

5.2. Theoretical Risk for Vulnerability to Particular Infections

Individuals genetically deficient in IL-12/IL-23 are particularly vulnerable to disseminated infections from mycobacteria (including nontuberculous, environmental mycobacteria), salmonella (including nontyphi strains), and Bacillus Calmette-Guerin (BCG) vaccinations. Serious infections and fatal outcomes have been reported in such patients.

It is not known whether patients with pharmacologic blockade of IL-12/IL-23 from treatment with ustekinumab products may be susceptible to these types of infections. Consider appropriate diagnostic testing (e.g., tissue culture, stool culture, as dictated by clinical circumstances).

5.3. Pre-treatment Evaluation for Tuberculosis

Evaluate patients for tuberculosis infection prior to initiating treatment with STEQEYMA.

Avoid administering STEQEYMA to patients with active tuberculosis infection. Initiate treatment of latent tuberculosis prior to administering STEQEYMA. Consider anti-tuberculosis therapy prior to initiation of STEQEYMA in patients with a past history of latent or active tuberculosis in whom an adequate course of treatment cannot be confirmed. Closely monitor patients receiving STEQEYMA for signs and symptoms of active tuberculosis during and after treatment.

5.4. Malignancies

Ustekinumab products are immunosuppressants and may increase the risk of malignancy. Malignancies were reported among subjects who received ustekinumab in clinical trials [see Adverse Reactions (6.1)]. In rodent models, inhibition of IL-12/IL-23p40 increased the risk of malignancy [see Nonclinical Toxicology (13)].

The safety of ustekinumab products has not been evaluated in patients who have a history of malignancy or who have a known malignancy.

There have been post-marketing reports of the rapid appearance of multiple cutaneous squamous cell carcinomas in patients receiving ustekinumab products who had pre-existing risk factors for developing non-melanoma skin cancer. Monitor all patients receiving STEQEYMA for the appearance of non-melanoma skin cancer. Closely follow patients greater than 60 years of age, those with a medical history of prolonged immunosuppressant therapy and those with a history of PUVA treatment [see Adverse Reactions (6.1)].

5.5. Hypersensitivity Reactions

Hypersensitivity reactions, including anaphylaxis and angioedema, have been reported with ustekinumab products [see Adverse Reactions (6.1, 6.3)]. If an anaphylactic or other clinically significant hypersensitivity reaction occurs, institute appropriate therapy and discontinue STEQEYMA.

5.6. Posterior Reversible Encephalopathy Syndrome (PRES)

Two cases of posterior reversible encephalopathy syndrome (PRES), also known as Reversible Posterior Leukoencephalopathy Syndrome (RPLS), were reported in clinical trials. Cases have also been reported in postmarketing experience in patients with psoriasis, psoriatic arthritis, and Crohn's disease. Clinical presentation included headaches, seizures, confusion, visual disturbances, and imaging changes consistent with PRES a few days to several months after ustekinumab product initiation. A few cases reported latency of a year or longer. Patients recovered with supportive care following withdrawal of ustekinumab products.

Monitor all patients treated with STEQEYMA for signs and symptoms of PRES. If PRES is suspected, promptly administer appropriate treatment and discontinue STEQEYMA.

5.7. Immunizations

Prior to initiating therapy with STEQEYMA, patients should receive all age-appropriate immunizations as recommended by current immunization guidelines. Patients being treated with STEQEYMA should avoid receiving live vaccines. Avoid administering BCG vaccines during treatment with STEQEYMA or for one year prior to initiating treatment or one year following discontinuation of treatment. Caution is advised when administering live vaccines to household contacts of patients receiving STEQEYMA because of the potential risk for shedding from the household contact and transmission to patient.

Non-live vaccinations received during a course of STEQEYMA may not elicit an immune response sufficient to prevent disease.

5.8. Noninfectious Pneumonia

Cases of interstitial pneumonia, eosinophilic pneumonia, and cryptogenic organizing pneumonia have been reported during post-approval use of ustekinumab products. Clinical presentations included cough, dyspnea, and interstitial infiltrates following one to three doses. Serious outcomes have included respiratory failure and prolonged hospitalization. Patients improved with discontinuation of therapy and in certain cases administration of corticosteroids. If diagnosis is confirmed, discontinue STEQEYMA and institute appropriate treatment [see Postmarketing Experience (6.3)].

6. ADVERSE REACTIONS

The following serious adverse reactions are discussed elsewhere in the label:

- Infections [see Warnings and Precautions (5.1)]
- Malignancies [see Warnings and Precautions (5.4)]
- Hypersensitivity Reactions [see Warnings and Precautions (5.5)]
- Posterior Reversible Encephalopathy Syndrome (PRES) [see Warnings and Precautions (5.6)]
- Noninfectious Pneumonia [see Warnings and Precautions (5.8)]

6.1. Clinical Trials Experience

Because clinical trials are conducted under widely varying conditions, adverse reaction rates observed in the clinical trials of a drug cannot be directly compared to rates in the clinical trials of another drug and may not reflect the rates observed in practice.

Adult Subjects with Plaque Psoriasis

The safety data reflect exposure to ustekinumab in 3117 adult subjects with plaque psoriasis, including 2414 exposed for at least 6 months, 1855 exposed for at least one year, 1653 exposed for at least two years, 1569 exposed for at least three years, 1482 exposed for at least four years and 838 exposed for at least five years.

Table 4 summarizes the adverse reactions that occurred at a rate of at least 1% with higher rates in the ustekinumab groups during the placebo-controlled period of Ps STUDY 1 and Ps STUDY 2 [see Clinical Studies (14)].

Table 4: Adverse Reactions Reported by ≥1% of Subjects with Plaque Psoriasis at Higher Rates in the ustekinumab groups through Week 12 in Ps STUDY 1 and Ps STUDY 2
 |  | Ustekinumab
 | Placebo | 45mg | 90mg
Subjects treated | 665 | 664 | 666
Nasopharyngitis | 51 (8%) | 56 (8%) | 49 (7%)
Upper respiratory tract infection | 30 (5%) | 36 (5%) | 28 (4%)
Headache | 23 (3%) | 33 (5%) | 32 (5%)
Fatigue | 14 (2%) | 18 (3%) | 17 (3%)
Back pain | 8 (1%) | 9 (1%) | 14 (2%)
Dizziness | 8 (1%) | 8 (1%) | 14 (2%)
Pharyngolaryngeal pain | 7 (1%) | 9 (1%) | 12 (2%)
Pruritus | 9 (1%) | 10 (2%) | 9 (1%)
Injection site erythema | 3 (<1%) | 6 (1%) | 13 (2%)
Myalgia | 4 (1%) | 7 (1%) | 8 (1%)
Depression | 3 (<1%) | 8 (1%) | 4 (1%)

Adverse reactions that occurred at rates less than 1% in the controlled period of Ps STUDIES 1 and 2 through week 12 included: cellulitis, herpes zoster, diverticulitis, and certain injection site reactions (pain, swelling, pruritus, induration, hemorrhage, bruising, and irritation).

One case of PRES occurred during adult plaque psoriasis clinical trials [see Warnings and Precautions (5.6)].

Infections

In the placebo-controlled period of clinical trials of subjects with plaque psoriasis (average follow-up of 12.6 weeks for placebo-treated subjects and 13.4 weeks for ustekinumab-treated subjects), 27% of ustekinumab-treated subjects reported infections (1.39 per subject-year of follow-up) compared with 24% of placebo-treated subjects (1.21 per subject-year of follow-up). Serious infections occurred in 0.3% of ustekinumab-treated subjects (0.01 per subject-year of follow-up) and in 0.4% of placebo-treated subjects (0.02 per subject-year of follow-up) [see Warnings and Precautions (5.1)].

In the controlled and non-controlled portions of plaque psoriasis clinical trials (median follow-up of 3.2 years), representing 8998 subject-years of exposure, 72.3% of ustekinumab-treated subjects reported infections (0.87 per subject-years of follow-up). Serious infections were reported in 2.8% of subjects (0.01 per subject-years of follow-up).

Malignancies

In the controlled and non-controlled portions of plaque psoriasis clinical trials (median follow-up of 3.2 years, representing 8998 subject-years of exposure), 1.7% of ustekinumab-treated subjects reported malignancies excluding non-melanoma skin cancers (0.60 per hundred subject-years of follow-up). Non-melanoma skin cancer was reported in 1.5% of ustekinumab-treated subjects (0.52 per hundred subject-years of follow-up) [see Warnings and Precautions (5.4)]. The most frequently observed malignancies other than non-melanoma skin cancer during the clinical trials were: prostate, melanoma, colorectal and breast. Malignancies other than non-melanoma skin cancer in ustekinumab-treated subjects during the controlled and uncontrolled portions of trials were similar in type and number to what would be expected in the general U.S. population according to the SEER database (adjusted for age, gender and race).^1

Pediatric Subjects with Plaque Psoriasis

The safety of ustekinumab was assessed in two trials of pediatric subjects with moderate to severe plaque psoriasis. Ps STUDY 3 evaluated safety for up to 60 weeks in 110 pediatric subjects 12 to 17 years old. Ps STUDY 4 evaluated safety for up to 56 weeks in 44 pediatric subjects 6 to 11 years old. The safety profile in pediatric subjects was similar to the safety profile from trials in adults with plaque psoriasis.

Psoriatic Arthritis

The safety of ustekinumab was assessed in 927 subjects in two randomized, double-blind, placebo- controlled trials in adults with active psoriatic arthritis (PsA). The overall safety profile of ustekinumab in subjects with PsA was consistent with the safety profile seen in adult psoriasis clinical trials. A higher incidence of arthralgia, nausea, and dental infections was observed in ustekinumab-treated subjects when compared with placebo-treated subjects (3% vs. 1% for arthralgia and 3% vs. 1% for nausea; 1% vs. 0.6% for dental infections) in the placebo-controlled portions of the PsA clinical trials.

Crohn's Disease

The safety of ustekinumab was assessed in 1407 subjects with moderately to severely active Crohn's disease (Crohn's Disease Activity Index [CDAI] greater than or equal to 220 and less than or equal to 450) in three randomized, double-blind, placebo-controlled, parallel-group, multicenter trials. These 1407 subjects included 40 subjects who received a prior investigational intravenous ustekinumab formulation but were not included in the efficacy analyses. In trials CD-1 and CD-2 there were 470 subjects who received ustekinumab 6 mg/kg as a weight-based single intravenous induction dose and 466 who received placebo [see Dosage and Administration (2.3)]. Subjects who were responders in either trial CD-1 or CD-2 were randomized to receive a subcutaneous maintenance regimen of either 90 mg ustekinumab every 8 weeks, or placebo for 44 weeks in trial CD-3. Subjects in these 3 trials may have received other concomitant therapies including aminosalicylates, immunomodulatory agents [azathioprine (AZA), 6-mercaptopurine (6-MP), methotrexate (MTX)], oral corticosteroids (prednisone or budesonide), and/or antibiotics for their Crohn's disease [see Clinical Studies (14.4)].

The overall safety profile of ustekinumab was consistent with the safety profile seen in the adult psoriasis and psoriatic arthritis clinical trials. Common adverse reactions in trials CD-1 and CD-2 and in trial CD-3 are listed in Tables 5 and 6, respectively.

Table 5: Common adverse reactions through Week 8 in Trials CD-1 and CD-2 occurring in ≥3% of Ustekinumab-treated subjects and higher than placebo
 |  | Placebo N=466 | Ustekinumab 6 mg/kg single intravenous induction dose N=470
Vomiting |  | 3% | 4%

Other less common adverse reactions reported in subjects in trials CD-1 and CD-2 included asthenia (1% vs 0.4%), acne (1% vs 0.4%), and pruritus (2% vs 0.4%).

Table 6: Common adverse reactions through Week 44 in Trial CD-3 occurring in ≥3% of Ustekinumab-treated subjects and higher than placebo
 | Placebo N=133 | Ustekinumab 90 mg subcutaneous maintenance dose every 8 weeks N=131
Nasopharyngitis | 8% | 11%
Injection site erythema | 0 | 5%
Vulvovaginal candidiasis/mycotic infection | 1% | 5%
Bronchitis | 3% | 5%
Pruritus | 2% | 4%
Urinary tract infection | 2% | 4%
Sinusitis | 2% | 3%

Infections

In subjects with Crohn's disease, serious or other clinically significant infections included anal abscess, gastroenteritis, and pneumonia. In addition, listeria meningitis and ophthalmic herpes zoster were reported in one patient each [see Warnings and Precautions (5.1)].

Malignancies

With up to one year of treatment in the Crohn's disease clinical trials, 0.2% of ustekinumab-treated subjects (0.36 events per hundred patient-years) and 0.2% of placebo-treated subjects (0.58 events per hundred patient-years) developed non-melanoma skin cancer.

Malignancies other than non-melanoma skin cancers occurred in 0.2% of ustekinumab-treated subjects (0.27 events per hundred patient-years) and in none of the placebo-treated subjects.

Hypersensitivity Reactions Including Anaphylaxis

In CD trials, two subjects reported hypersensitivity reactions following ustekinumab administration. One patient experienced signs and symptoms consistent with anaphylaxis (tightness of the throat, shortness of breath, and flushing) after a single subcutaneous administration (0.1% of subjects receiving subcutaneous ustekinumab). In addition, one subject experienced signs and symptoms consistent with or related to a hypersensitivity reaction (chest discomfort, flushing, urticaria, and increased body temperature) after the initial intravenous ustekinumab dose (0.08% of subjects receiving intravenous ustekinumab). These subjects were treated with oral antihistamines or corticosteroids and in both cases symptoms resolved within an hour.

Ulcerative Colitis

The safety of ustekinumab was evaluated in two randomized, double-blind, placebo-controlled clinical trials (UC-1 [IV induction] and UC-2 [SC maintenance]) in 960 adult subjects with moderately to severely active ulcerative colitis [see Clinical Studies (14.5)]. The overall safety profile of ustekinumab in subjects with ulcerative colitis was consistent with the safety profile seen across all approved indications. Adverse reactions reported in at least 3% of ustekinumab-treated subjects and at a higher rate than placebo were:

- Induction (UC-1): nasopharyngitis (7% vs 4%).
- Maintenance (UC-2): nasopharyngitis (24% vs 20%), headache (10% vs 4%), abdominal
  pain (7% vs 3%), influenza (6% vs 5%), fever (5% vs. 4%), diarrhea (4% vs 1%), sinusitis
  (4% vs 1%), fatigue (4% vs 2%), and nausea (3% vs 2%).

Infections

In subjects with ulcerative colitis, serious or other clinically significant infections included gastroenteritis and pneumonia. In addition, listeriosis and ophthalmic herpes zoster were reported in one subject each [see Warnings and Precautions (5.1)].

Malignancies

With up to one year of treatment in the ulcerative colitis clinical trials, 0.4% of ustekinumab- treated subjects (0.48 events per hundred patient-years) and 0.0% of placebo-treated subjects (0.00 events per hundred patient-years) developed non-melanoma skin cancer. Malignancies other than non-melanoma skin cancers occurred in 0.5% of ustekinumab-treated subjects (0.64 events per hundred patient-years) and 0.2% of placebo-treated subjects (0.40 events per hundred patient- years).

6.2. Immunogenicity

The observed incidence of anti-drug antibodies is highly dependent on the sensitivity and specificity of the assay. Differences in assay methods preclude meaningful comparisons of the incidence of anti-drug antibodies in the studies described below with the incidence of anti-drug antibodies in other studies, including those of ustekinumab or of other ustekinumab products.

Approximately 6 to 12.4% of subjects treated with ustekinumab in plaque psoriasis and psoriatic arthritis clinical trials developed antibodies to ustekinumab, which were generally low-titer. In plaque psoriasis clinical trials, antibodies to ustekinumab were associated with reduced or undetectable serum ustekinumab concentrations and reduced efficacy. In plaque psoriasis trials, the majority of subjects who were positive for antibodies to ustekinumab had neutralizing antibodies.

In Crohn's disease and ulcerative colitis clinical trials, 2.9% and 4.6% of subjects, respectively, developed antibodies to ustekinumab when treated with ustekinumab for approximately one year. No apparent association between the development of antibodies to ustekinumab and the development of injection site reactions was seen.

6.3. Postmarketing Experience

The following adverse reactions have been reported during post-approval use of ustekinumab products. Because these reactions are reported voluntarily from a population of uncertain size, it is not always possible to reliably estimate their frequency or establish a causal relationship to ustekinumab product exposure.

Immune system disorders: Serious hypersensitivity reactions (including anaphylaxis and angioedema), other hypersensitivity reactions (including rash and urticaria).

Infections and infestations: Lower respiratory tract infection (including opportunistic fungal infections and tuberculosis).

Neurological disorders: Posterior Reversible Encephalopathy Syndrome (PRES).

Respiratory, thoracic and mediastinal disorders: Interstitial pneumonia, eosinophilic pneumonia, and cryptogenic organizing pneumonia.

Skin reactions: Pustular psoriasis, erythrodermic psoriasis, hypersensitivity vasculitis.

7. DRUG INTERACTIONS

7.1. Concomitant Therapies

In plaque psoriasis trials the safety of ustekinumab products in combination with immunosuppressive agents or phototherapy has not been evaluated. In psoriatic arthritis trials, concomitant MTX use did not appear to influence the safety or efficacy of ustekinumab. In Crohn's disease and ulcerative colitis induction trials, immunomodulators (6-MP, AZA, MTX) were used concomitantly in approximately 30% of subjects and corticosteroids were used concomitantly in approximately 40% and 50% of Crohn's disease and ulcerative colitis subjects, respectively. Use of these concomitant therapies did not appear to influence the overall safety or efficacy of ustekinumab.

7.2. CYP450 Substrates

The formation of CYP450 enzymes can be suppressed by increased levels of certain cytokines (e.g., IL-1, IL-6, TNFα, IFN) during chronic inflammation. Thus, use of ustekinumab products, antagonists of IL-12 and IL-23, could normalize the formation of CYP450 enzymes. Upon initiation or discontinuation of STEQEYMA in patients who are receiving concomitant CYP450 substrates, particularly those with a narrow therapeutic index, consider monitoring for therapeutic effect or drug concentration and adjust the individual dosage of the CYP substrate as needed. See the prescribing information of specific CYP substrates.

A CYP-mediated drug interaction effect was not observed in subjects with Crohn's disease [see Clinical Pharmacology (12.3)].

7.3. Allergen Immunotherapy

Ustekinumab products have not been evaluated in patients who have undergone allergy immunotherapy. Ustekinumab products may decrease the protective effect of allergen immunotherapy (decrease tolerance) which may increase the risk of an allergic reaction to a dose of allergen immunotherapy. Therefore, caution should be exercised in patients receiving or who have received allergen immunotherapy, particularly for anaphylaxis.

8. USE IN SPECIFIC POPULATIONS

8.1. Pregnancy

Risk Summary

Limited data from observational studies, published case reports, and postmarketing surveillance on the use of ustekinumab products during pregnancy are insufficient to inform a drug associated risk of major birth defects, miscarriage, and other adverse maternal or fetal outcomes. Transport of human IgG antibody across the placenta increases as pregnancy progresses and peaks during the third trimester; therefore, ustekinumab products may be transferred to the developing fetus [see Clinical Considerations]. In animal reproductive and developmental toxicity studies, no adverse developmental effects were observed in offspring after administration of ustekinumab to pregnant monkeys at exposures greater than 100 times the maximum recommended human dose (MRHD).

The background risk of major birth defects and miscarriage for the indicated population(s) are unknown. All pregnancies have a background risk of birth defect, loss, or other adverse outcomes. In the U.S. general population, the estimated background risk of major birth defects and miscarriage of clinically recognized pregnancies is 2% to 4% and 15% to 20%, respectively.

Clinical Considerations

Fetal/Neonatal Adverse Reactions

Because ustekinumab products may theoretically interfere with immune response to infections, consider risks and benefits prior to administering live vaccines to infants exposed to STEQEYMA in utero. There are insufficient data regarding exposed infant serum levels of ustekinumab products at birth and the duration of persistence of ustekinumab products in infant serum after birth. Although a specific timeframe to delay administration of live attenuated vaccines in infants exposed in utero is unknown, consider the risks and benefits of delaying a minimum of 6 months after birth because of the clearance of the product.

Data

Animal Data

Ustekinumab was tested in two embryo-fetal development toxicity studies in cynomolgus monkeys. No teratogenic or other adverse developmental effects were observed in fetuses from pregnant monkeys that were administered ustekinumab subcutaneously twice weekly or intravenously weekly during the period of organogenesis. Serum concentrations of ustekinumab in pregnant monkeys were greater than 100 times the serum concentration in patients treated subcutaneously with 90 mg of ustekinumab weekly for 4 weeks.

In a combined embryo-fetal development and pre- and post-natal development toxicity study, pregnant cynomolgus monkeys were administered subcutaneous doses of ustekinumab twice weekly at exposures greater than 100 times the MRHD from the beginning of organogenesis to Day 33 after delivery. Neonatal deaths occurred in the offspring of one monkey administered ustekinumab at 22.5 mg/kg and one monkey dosed at 45 mg/kg. No ustekinumab-related-effects on functional, morphological, or immunological development were observed in the neonates from birth through six months of age.

8.2. Lactation

Risk Summary

Limited data from published literature suggests that ustekinumab is present in human breast milk. There are no available data on the effects of ustekinumab products on milk production. The effects of local gastrointestinal exposure and limited systemic exposure in the breastfed infant to ustekinumab products are unknown. No adverse effects on the breastfed infant causally related to ustekinumab products have been identified in the published literature or postmarketing experience.

The developmental and health benefits of breastfeeding should be considered along with the mother's clinical need for STEQEYMA and any potential adverse effects on the breastfed child from STEQEYMA or from the underlying maternal condition.

8.4. Pediatric Use

Plaque Psoriasis

The safety and effectiveness of STEQEYMA have been established for the treatment of moderate to severe plaque psoriasis in pediatric patients 6 to 17 years of age who are candidates for phototherapy or systemic therapy.

Use of STEQEYMA in pediatric patients 12 to less than 17 years of age is supported by evidence from a multicenter, randomized, 60week trial (Ps STUDY 3) of ustekinumab that included a 12-week, double-blind, placebo-controlled, parallel group portion, in 110 pediatric subjects 12 years of age and older [see Adverse Reactions (6.1), Clinical Studies (14.2)].

Use of STEQEYMA in pediatric patients 6 to 11 years of age is supported by evidence from an open-label, single-arm, efficacy, safety, and pharmacokinetics trial (Ps STUDY 4) of ustekinumab in 44 subjects [see Adverse Reactions (6.1), Pharmacokinetics (12.3)].

The safety and effectiveness of STEQEYMA have not been established in pediatric patients less than 6 years of age with plaque psoriasis.

Psoriatic Arthritis

The safety and effectiveness of STEQEYMA have been established for treatment of psoriatic arthritis in pediatric patients 6 to 17 years old.

Use of STEQEYMA in these age groups is supported by evidence from adequate and well controlled trials of ustekinumab in adults with psoriasis and PsA, pharmacokinetic data from adult subjects with psoriasis, adult subjects with PsA and pediatric subjects with psoriasis, and safety data of ustekinumab from two clinical trials in 44 pediatric subjects 6 to 11 years old with psoriasis and 110 pediatric subjects 12 to 17 years old with psoriasis. The observed pre-dose (trough) concentrations are generally comparable between adult subjects with psoriasis, adult subjects with PsA and pediatric subjects with psoriasis, and the PK exposure is expected to be comparable between adult and pediatric subjects with PsA [see Adverse Reactions (6.1), Clinical Pharmacology (12.3), and Clinical Studies (14.1, 14.2, 14.3)].

The safety and effectiveness of STEQEYMA have not been established in pediatric patients less than 6 years old with psoriatic arthritis.

Crohn's Disease and Ulcerative Colitis

The safety and effectiveness of STEQEYMA have not been established in pediatric patients with Crohn's disease or ulcerative colitis.

8.5. Geriatric Use

Of the 6709 subjects exposed to ustekinumab, a total of 340 were 65 years of age or older (183 subjects with plaque psoriasis, 65 subjects with psoriatic arthritis, 58 subjects with Crohn's disease, and 34 subjects with ulcerative colitis), and 40 subjects were 75 years of age or older. Clinical trials of ustekinumab did not include sufficient numbers of subjects 65 years of age and older to determine whether they respond differently from younger adult subjects.

10. OVERDOSAGE

Single doses up to 6 mg/kg intravenously have been administered in clinical trials without dose-limiting toxicity. In case of overdosage, monitor the patient for any signs or symptoms of adverse reactions or effects and institute appropriate symptomatic treatment immediately. Consider contacting the Poison Help line (1-800-222-1222) or a medical toxicologist for additional overdose management recommendations.

11. DESCRIPTION

Ustekinumab-stba, a human IgG1κ monoclonal antibody, is a human interleukin-12 and -23 antagonist. Using DNA recombinant technology, ustekinumab-stba is produced in a Chinese Hamster Ovary (CHO) cell line. The manufacturing process contains steps for the clearance of viruses. Ustekinumab-stba is comprised of 1326 amino acids and has an estimated molecular mass that ranges from 148,079 to 149,690 Daltons.

STEQEYMA (ustekinumab-stba) injection is a sterile, preservative-free, colorless to pale yellow solution and may contain a few small translucent or white particles with pH of 5.7.

STEQEYMA for Subcutaneous Use

Available as 45 mg of ustekinumab-stba in 0.5 mL and 90 mg of ustekinumab-stba in 1 mL, supplied as a sterile solution in a single-dose prefilled syringe with a 27 gauge fixed ½ inch needle. The syringe is fitted with a passive needle guard and a needle cover.

Each 0.5 mL prefilled syringe delivers 45 mg ustekinumab-stba, histidine (0.18 mg), L-histidine monohydrochloride monohydrate (0.46 mg), polysorbate 80 (0.02 mg), sucrose (38 mg), and Water for Injection.

Each 1 mL prefilled syringe delivers 90 mg ustekinumab-stba, histidine (0.36 mg), L-histidine monohydrochloride monohydrate (0.91 mg), polysorbate 80 (0.04 mg), sucrose (76 mg), and Water for Injection.

STEQEYMA for Intravenous Infusion

Available as 130 mg of ustekinumab-stba in 26 mL, supplied as a single-dose 30 mL Type I glass vial with a coated stopper.

Each 26 mL vial delivers 130 mg ustekinumab-stba, edetate disodium (0.47 mg), histidine (9.36 mg), L-histidine monohydrochloride monohydrate (23.66 mg), methionine (10.56 mg), polysorbate 80 (10.37 mg), sucrose (1,976 mg), and Water for Injection.

12. CLINICAL PHARMACOLOGY

12.1. Mechanism of Action

Ustekinumab products are human IgG1қ monoclonal antibodies that bind with specificity to the p40 protein subunit used by both the IL-12 and IL-23 cytokines. IL-12 and IL-23 are naturally occurring cytokines that are involved in inflammatory and immune responses, such as natural killer cell activation and CD4+ T-cell differentiation and activation. In in vitro models, ustekinumab products were shown to disrupt IL-12 and IL-23 mediated signaling and cytokine cascades by disrupting the interaction of these cytokines with a shared cell-surface receptor chain, IL-12Rβ1. The cytokines IL-12 and IL-23 have been implicated as important contributors to the chronic inflammation that is a hallmark of Crohn's disease and ulcerative colitis. In animal models of colitis, genetic absence or antibody blockade of the p40 subunit of IL-12 and IL-23, the target of ustekinumab products, was shown to be protective.

12.2. Pharmacodynamics

Plaque Psoriasis

In a small exploratory trial, a decrease was observed in the expression of mRNA of its molecular targets IL-12 and IL-23 in lesional skin biopsies measured at baseline and up to two weeks post-treatment in subjects with plaque psoriasis.

Ulcerative Colitis

In both trial UC-1 (induction) and trial UC-2 (maintenance), a positive relationship was observed between exposure and rates of clinical remission, clinical response, and endoscopic improvement. The response rate approached a plateau at the ustekinumab exposures associated with the recommended dosing regimen for maintenance treatment [see Clinical Studies (14.5)].

12.3. Pharmacokinetics

Absorption

In adult subjects with plaque psoriasis, the median time to reach the maximum serum concentration (Tmax) was 13.5 days and 7 days, respectively, after a single subcutaneous administration of 45 mg (N=22) and 90 mg (N=24) of ustekinumab. In healthy subjects (N=30), the median Tmax value (8.5 days) following a single subcutaneous administration of 90 mg of ustekinumab was comparable to that observed in subjects with plaque psoriasis.

Following multiple subcutaneous doses of ustekinumab in adult subjects with plaque psoriasis, steady- state serum concentrations of ustekinumab were achieved by Week 28. The mean (±SD) steady- state trough serum ustekinumab concentrations were 0.69 ± 0.69 mcg/mL for subjects less than or equal to 100 kg receiving a 45 mg dose and 0.74 ± 0.78 mcg/mL for subjects greater than 100 kg receiving a 90 mg dose. There was no apparent accumulation in serum ustekinumab concentration over time when given subcutaneously every 12 weeks.

Following the recommended intravenous induction dose, mean ±SD peak serum ustekinumab concentration was 125.2 ± 33.6 mcg/mL in subjects with Crohn's disease, and 129.1 ± 27.6 mcg/mL in subjects with ulcerative colitis. Starting at Week 8, the recommended subcutaneous maintenance dosing of 90 mg ustekinumab was administered every 8 weeks. Steady state ustekinumab concentration was achieved by the start of the second maintenance dose. There was no apparent accumulation in ustekinumab concentration over time when given subcutaneously every 8 weeks. Mean ±SD steady-state trough concentration was 2.5 ± 2.1 mcg/mL in subjects with Crohn's disease, and 3.3 ± 2.3 mcg/mL in subjects with ulcerative colitis for 90 mg ustekinumab administered every 8 weeks.

Distribution

Population pharmacokinetic analyses showed that the volume of distribution of ustekinumab in the central compartment was 2.7 L (95% CI: 2.69, 2.78) in subjects with Crohn's disease and 3.0 L (95% CI: 2.96, 3.07) in subjects with ulcerative colitis. The total volume of distribution at steady- state was 4.6 L in subjects with Crohn's disease and 4.4 L in subjects with ulcerative colitis.

Elimination

The mean (±SD) half-life ranged from 14.9 ± 4.6 to 45.6 ± 80.2 days across all plaque psoriasis trials following subcutaneous administration. Population pharmacokinetic analyses showed that the clearance of ustekinumab was 0.19 L/day (95% CI: 0.185, 0.197) in subjects with Crohn's disease and 0.19 L/day (95% CI: 0.179, 0.192) in subjects with ulcerative colitis with an estimated median terminal half-life of approximately 19 days for both IBD (Crohn's disease and ulcerative colitis) populations.

These results indicate the pharmacokinetics of ustekinumab were similar between subjects with Crohn's disease and ulcerative colitis.

Metabolism

The metabolic pathway of ustekinumab products has not been characterized. As a human IgG1κ monoclonal antibody, ustekinumab products are expected to be degraded into small peptides and amino acids via catabolic pathways in the same manner as endogenous IgG.

Specific Populations

Weight

When given the same dose, subjects with plaque psoriasis or psoriatic arthritis weighing more than 100 kg had lower median serum ustekinumab concentrations compared with those subjects weighing 100 kg or less. The median trough serum concentrations of ustekinumab in subjects of higher weight (greater than 100 kg) in the 90 mg group were comparable to those in subjects of lower weight (100 kg or less) in the 45 mg group.

Age: Geriatric Population

A population pharmacokinetic analysis (N=106/1937 subjects with plaque psoriasis greater than or equal to 65 years old) was performed to evaluate the effect of age on the pharmacokinetics of ustekinumab. There were no apparent changes in pharmacokinetic parameters (clearance and volume of distribution) in subjects older than 65 years old.

Age: Pediatric Population

Following multiple recommended doses of ustekinumab in pediatric subjects 6 to 17 years of age with plaque psoriasis, steady-state serum concentrations of ustekinumab were achieved by Week 28. At Week 28, the mean ±SD steady-state trough serum ustekinumab concentrations were 0.36 ± 0.26 mcg/mL and 0.54 ± 0.43 mcg/mL, respectively, in pediatric subjects 6 to 11 years of age and pediatric subjects 12 to 17 years of age.

Overall, the observed steady-state ustekinumab trough concentrations in pediatric subjects with plaque psoriasis were within the range of those observed for adult subjects with plaque psoriasis and adult subjects with PsA after administration of ustekinumab.

Drug Interaction Studies

The effects of IL-12 or IL-23 on the regulation of CYP450 enzymes were evaluated in an in vitro study using human hepatocytes, which showed that IL-12 and/or IL-23 at levels of 10 ng/mL did not alter human CYP450 enzyme activities (CYP1A2, 2B6, 2C9, 2C19, 2D6, or 3A4).

No clinically significant changes in exposure of caffeine (CYP1A2 substrate), warfarin (CYP2C9 substrate), omeprazole (CYP2C19 substrate), dextromethorphan (CYP2D6 substrate), or midazolam (CYP3A substrate) were observed when used concomitantly with ustekinumab at the approved recommended dosage in subjects with Crohn's disease [see Drug Interactions (7.2)].

Population pharmacokinetic analyses indicated that the clearance of ustekinumab was not impacted by concomitant MTX, NSAIDs, and oral corticosteroids, or prior exposure to a TNF blocker in subjects with psoriatic arthritis.

In subjects with Crohn's disease and ulcerative colitis, population pharmacokinetic analyses did not indicate changes in ustekinumab clearance with concomitant use of corticosteroids or immunomodulators (AZA, 6-MP, or MTX); and serum ustekinumab concentrations were not impacted by concomitant use of these medications.

13. NONCLINICAL TOXICOLOGY

13.1. Carcinogenesis, Mutagenesis, Impairment of Fertility

Animal studies have not been conducted to evaluate the carcinogenic or mutagenic potential of ustekinumab products. Published literature showed that administration of murine IL-12 caused an anti- tumor effect in mice that contained transplanted tumors and IL-12/IL-23p40 knockout mice or mice treated with anti-IL-12/IL-23p40 antibody had decreased host defense to tumors. Mice genetically manipulated to be deficient in both IL-12 and IL-23 or IL-12 alone developed UV- induced skin cancers earlier and more frequently compared to wild-type mice. The relevance of these experimental findings in mouse models for malignancy risk in humans is unknown.

No effects on fertility were observed in male cynomolgus monkeys that were administered ustekinumab at subcutaneous doses up to 45 mg/kg twice weekly (45 times the MRHD on a mg/kg basis) prior to and during the mating period. However, fertility and pregnancy outcomes were not evaluated in mated females.

No effects on fertility were observed in female mice that were administered an analogous IL-12/IL- 23p40 antibody by subcutaneous administration at doses up to 50 mg/kg, twice weekly, prior to and during early pregnancy.

13.2. Animal Toxicology and/or Pharmacology

In a 26-week toxicology study, one out of 10 monkeys subcutaneously administered 45 mg/kg ustekinumab twice weekly for 26 weeks had a bacterial infection.

14. CLINICAL STUDIES

14.1. Adult Plaque Psoriasis

Two multicenter, randomized, double-blind, placebo-controlled trials (Ps STUDY 1 and Ps STUDY 2) enrolled a total of 1996 subjects 18 years of age and older with plaque psoriasis who had a minimum body surface area involvement of 10%, and Psoriasis Area and Severity Index (PASI) score ≥12, and who were candidates for phototherapy or systemic therapy. Subjects with guttate, erythrodermic, or pustular psoriasis were excluded from the trials.

Ps STUDY 1 enrolled 766 subjects and Ps STUDY 2 enrolled 1230 subjects. The trials had the same design through Week 28. In both trials, subjects were randomized in equal proportion to placebo, 45 mg or 90 mg of ustekinumab. Subjects randomized to ustekinumab received 45 mg or 90 mg doses, regardless of weight, at Weeks 0, 4, and 16. Subjects randomized to receive placebo at Weeks 0 and 4 crossed over to receive ustekinumab (either 45 mg or 90 mg) at Weeks 12 and 16.

In both trials, subjects in all treatment groups had a median baseline PASI score ranging from approximately 17 to 18. Baseline PGA score was marked or severe in 44% of subjects in Ps STUDY 1 and 40% of subjects in Ps STUDY 2. Approximately two-thirds of all subjects had received prior phototherapy, 69% had received either prior conventional systemic or biologic therapy for the treatment of psoriasis, with 56% receiving prior conventional systemic therapy and 43% receiving prior biologic therapy. A total of 28% of subjects had a history of psoriatic arthritis.

In both trials, the endpoints were the proportion of subjects who achieved at least a 75% reduction in PASI score (PASI 75) from baseline to Week 12 and treatment success (cleared or minimal) on the Physician's Global Assessment (PGA). The PGA is a 6-category scale ranging from 0 (cleared) to 5 (severe) that indicates the physician's overall assessment of psoriasis focusing on plaque thickness/induration, erythema, and scaling.

Clinical Response

The results of Ps STUDY 1 and Ps STUDY 2 are presented in Table 7 below.

Table 7: Clinical Outcomes at Week 12 in Adults with Plaque Psoriasis in Ps STUDY 1 and Ps STUDY 2
 | Ps STUDY 1 |  |  | Ps STUDY 2
 |  | Ustekinumab |  |  | Ustekinumab
 | Placebo | 45 mg | 90 mg | Placebo | 45 mg | 90 mg
Subjects randomized | 255 | 255 | 256 | 410 | 409 | 411
PASI 75 response | 8 (3%) | 171 (67%) | 170 (66%) | 15 (4%) | 273 (67%) | 311 (76%)
PGA of Cleared or Minimal | 10 (4%) | 151 (59%) | 156 (61%) | 18 (4%) | 277 (68%) | 300 (73%)

Examination of age, gender, and race subgroups did not identify differences in response to ustekinumab among these subgroups.

In subjects who weighed 100 kg or less, response rates were comparable with both the 45 mg and 90 mg doses; however, in subjects who weighed greater than 100 kg, higher response rates were seen with 90 mg dosing compared with 45 mg dosing (Table 8 below).

Table 8: Clinical Outcomes by Weight at Week 12 in Adults with Plaque Psoriasis in Ps STUDY 1 and Ps STUDY 2
 | Ps STUDY 1 |  |  | Ps STUDY 2
 |  | Ustekinumab |  |  | Ustekinumab
 | Placebo | 45 mg | 90 mg | Placebo | 45 mg | 90 mg
Subjects randomized PASI 75 response [Subjects were dosed with trial medication at Weeks 0 and 4.] | 255 | 255 | 256 | 410 | 409 | 411
≤100 kg | 4% 6/166 | 74% 124/168 | 65% 107/164 | 4% 12/290 | 73% 218/297 | 78% 225/289
>100 kg | 2% 2/89 | 54% 47/87 | 68% 63/92 | 3% 3/120 | 49% 55/112 | 71% 86/121
PGA of Cleared or Minimal
≤100 kg | 4% 7/166 | 64% 108/168 | 63% 103/164 | 5% 14/290 | 74% 220/297 | 75% 216/289
>100 kg | 3% 3/89 | 49% 43/87 | 58% 53/92 | 3% 4/120 | 51% 57/112 | 69% 84/121

Subjects in Ps STUDY 1 who were PASI 75 responders at both Weeks 28 and 40 were re- randomized at Week 40 to either continued dosing of ustekinumab (ustekinumab at Week 40) or to withdrawal of therapy (placebo at Week 40). At Week 52, 89% (144/162) of subjects re-randomized to ustekinumab treatment were PASI 75 responders compared with 63% (100/159) of subjects re-randomized to placebo (treatment withdrawal after Week 28 dose). The median time to loss of PASI 75 response among the subjects randomized to treatment withdrawal was 16 weeks.

14.2. Pediatric Plaque Psoriasis

A multicenter, randomized, double blind, placebo-controlled trial (Ps STUDY 3) enrolled 110 pediatric subjects 12 to 17 years of age with a minimum BSA involvement of 10%, a PASI score greater than or equal to 12, and a PGA score greater than or equal to 3, who were candidates for phototherapy or systemic therapy and whose disease was inadequately controlled by topical therapy.

Subjects were randomized to receive placebo (n = 37), the recommended dose of ustekinumab (n = 36), or one-half the recommended dose of ustekinumab (n = 37) by subcutaneous injection at Weeks 0 and 4 followed by dosing every 12 weeks (q12w). The recommended dose of ustekinumab was 0.75 mg/kg for subjects weighing less than 60 kg, 45 mg for subjects weighing 60 kg to 100 kg, and 90 mg for subjects weighing greater than 100 kg. At Week 12, subjects who received placebo were crossed over to receive ustekinumab at the recommended dose or one-half the recommended dose.

Of the pediatric subjects, approximately 63% had prior exposure to phototherapy or conventional systemic therapy and approximately 11% had prior exposure to biologics.

The endpoints were the proportion of subjects who achieved a PGA score of cleared (0) or minimal (1), PASI 75, and PASI 90 at Week 12. Subjects were followed for up to 60 weeks following first administration of trial agent.

Clinical Response

The efficacy results at Week 12 for Ps STUDY 3 are presented in Table 9.

Table 9: Efficacy Results at Week 12 in Pediatric Subjects 12 to 17 years with Plaque Psoriasis in Ps STUDY 3
 | Ps STUDY 3
 | Placebo n (%) | Ustekinumab [Using the weight-based dosage regimen specified in Table 1.] n (%)
N | 37 | 36
PGA
PGA of cleared (0) or minimal (1) | 2 (5.4%) | 25 (69.4%)
PASI
PASI 75 responders | 4 (10.8%) | 29 (80.6%)
PASI 90 responders | 2 (5.4%) | 22 (61.1%)

14.3. Psoriatic Arthritis

The safety and efficacy of ustekinumab was assessed in 927 subjects (PsA STUDY 1, n=615; PsA STUDY 2, n=312), in two randomized, double-blind, placebo-controlled trials in adult subjects 18 years of age and older with active PsA (≥5 swollen joints and ≥5 tender joints) despite nonsteroidal anti-inflammatory (NSAID) or disease modifying antirheumatic (DMARD) therapy. Subjects in these trials had a diagnosis of PsA for at least 6 months. Subjects with each subtype of PsA were enrolled, including polyarticular arthritis with the absence of rheumatoid nodules (39%), spondylitis with peripheral arthritis (28%), asymmetric peripheral arthritis (21%), distal interphalangeal involvement (12%) and arthritis mutilans (0.5%). Over 70% and 40% of the subjects, respectively, had enthesitis and dactylitis at baseline.

Subjects were randomized to receive treatment with ustekinumab 45 mg, 90 mg, or placebo subcutaneously at Weeks 0 and 4 followed by every 12 weeks (q12w) dosing. Approximately 50% of subjects continued on stable doses of MTX (≤25 mg/week). The primary endpoint was the percentage of subjects achieving ACR 20 response at Week 24.

In PsA STUDY 1 and PsA STUDY 2, 80% and 86% of the subjects, respectively, had been previously treated with DMARDs. In PsA STUDY 1, previous treatment with anti-tumor necrosis factor (TNF)-α agent was not allowed. In PsA STUDY 2, 58% (n=180) of the subjects had been previously treated with TNF blocker, of whom over 70% had discontinued their TNF blocker treatment for lack of efficacy or intolerance at any time.

Clinical Response

In both trials, a greater proportion of subjects achieved ACR 20, ACR 50 and PASI 75 response in the ustekinumab 45 mg and 90 mg groups compared to placebo at Week 24 (see Table 10). ACR 70 responses were also higher in the ustekinumab 45 mg and 90 mg groups, although the difference was only numerical (p=NS) in STUDY 2. Responses were consistent in subjects treated with ustekinumab alone or in combination with methotrexate. Responses were similar in subjects regardless of prior TNFα exposure.

Table 10: ACR 20, ACR 50, ACR 70 and PASI 75 responses in PsA STUDY 1 and PsA STUDY 2 at Week 24
 | PsA STUDY 1 |  |  | PsA STUDY 2
 |  | Ustekinumab |  |  | Ustekinumab
 | Placebo | 45 mg | 90 mg | Placebo | 45 mg | 90 mg
Number of subjects randomized | 206 | 205 | 204 | 104 | 103 | 105
ACR 20 response, N (%) | 47 (23%) | 87 (42%) | 101 (50%) | 21 (20%) | 45 (44%) | 46 (44%)
ACR 50 response, N (%) | 18 (9%) | 51 (25%) | 57 (28%) | 7 (7%) | 18 (17%) | 24 (23%)
ACR 70 response, N (%) | 5 (2%) | 25 (12%) | 29 (14%) | 3 (3%) | 7 (7%) | 9 (9%)
Number of subjects with ≥ 3% BSA [Number of subjects with ≥ 3% BSA psoriasis skin involvement at baseline] | 146 | 145 | 149 | 80 | 80 | 81
PASI 75 response, N (%) | 16 (11%) | 83 (57%) | 93 (62%) | 4 (5%) | 41 (51%) | 45 (56%)

The percent of subjects achieving ACR 20 responses by visit is shown in Figure 1.

Figure 1: Percent of subjects achieving ACR 20 response through Week 24

The results of the components of the ACR response criteria are shown in Table 11.

Table 11: Mean change from baseline in ACR components at Week 24
 | PsA STUDY 1
 | Placebo (N = 206) | Ustekinumab
 | Placebo (N = 206) | 45 mg (N = 205) | 90 mg (N = 204)
Number of swollen joints [Number of swollen joints counted (0-66)]
Baseline | 15 | 12 | 13
Mean Change at Week 24 | -3 | -5 | -6
Number of tender joints [Number of tender joints counted (0-68)]
Baseline | 25 | 22 | 23
Mean Change at Week 24 | -4 | -8 | -9
Subject's assessment of pain [Visual analogue scale; 0= best, 10=worst.]
Baseline | 6.1 | 6.2 | 6.6
Mean Change at Week 24 | -0.5 | -2.0 | -2.6
Subject global assessment
Baseline | 6.1 | 6.3 | 6.4
Mean Change at Week 24 | -0.5 | -2.0 | -2.5
Physician global assessment
Baseline | 5.8 | 5.7 | 6.1
Mean Change at Week 24 | -1.4 | -2.6 | -3.1
Disability index (HAQ) [Disability Index of the Health Assessment Questionnaire; 0 = best, 3 = worst, measures the patient's ability to perform the following: dress/groom, arise, eat, walk, reach, grip, maintain hygiene, and maintain daily activity.]
Baseline | 1.2 | 1.2 | 1.2
Mean Change at Week 24 | -0.1 | -0.3 | -0.4
CRP (mg/dL) [CRP: (Normal Range 0.0-1.0 mg/dL)]
Baseline | 1.6 | 1.7 | 1.8
Mean Change at Week 24 | 0.01 | -0.5 | -0.8

An improvement in enthesitis and dactylitis scores was observed in each ustekinumab group compared with placebo at Week 24.

Physical Function

Ustekinumab-treated subjects showed improvement in physical function compared to subjects treated with placebo as assessed by HAQ-DI at Week 24. In both trials, the proportion of HAQ- DI responders (≥0.3 improvement in HAQ-DI score) was greater in the ustekinumab 45 mg and 90 mg groups compared to placebo at Week 24.

14.4. Crohn's Disease

Ustekinumab was evaluated in three randomized, double-blind, placebo-controlled clinical trials in adult subjects with moderately to severely active Crohn's disease (Crohn's Disease Activity Index [CDAI] score of 220 to 450). There were two 8-week intravenous induction trials (CD-1 and CD-2) followed by a 44-week subcutaneous randomized withdrawal maintenance trial (CD- 3) representing 52 weeks of therapy. Subjects in CD-1 had failed or were intolerant to treatment with one or more TNF blockers, while subjects in CD-2 had failed or were intolerant to treatment with immunomodulators or corticosteroids, but never failed treatment with a TNF blocker.

Trials CD-1 and CD-2

In trials CD-1 and CD-2, 1409 subjects were randomized, of whom 1368 (CD-1, n=741; CD-2, n=627) were included in the final efficacy analysis. Induction of clinical response (defined as a reduction in CDAI score of greater than or equal to 100 points or CDAI score of less than 150) at Week 6 and clinical remission (defined as a CDAI score of less than 150) at Week 8 were evaluated. In both trials, subjects were randomized to receive a single intravenous administration of ustekinumab at either approximately 6 mg/kg, placebo (see Table 3), or 130 mg (a lower dose than recommended).

In trial CD-1, subjects had failed or were intolerant to prior treatment with a TNF blocker: 29% subjects had an inadequate initial response (primary non-responders), 69% responded but subsequently lost response (secondary non-responders) and 36% were intolerant to a TNF blocker. Of these subjects, 48% failed or were intolerant to one TNF blocker and 52% had failed 2 or 3 prior TNF blockers. At baseline and throughout the trial, approximately 46% of the subjects were receiving corticosteroids and 31% of the subjects were receiving immunomodulators (AZA, 6-MP, MTX). The median baseline CDAI score was 319 in the ustekinumab approximately 6 mg/kg group and 313 in the placebo group.

In trial CD-2, subjects had failed or were intolerant to prior treatment with corticosteroids (81% of subjects), at least one immunomodulator (6-MP, AZA, MTX; 68% of subjects), or both (49% of subjects). Additionally, 69% never received a TNF blocker and 31% previously received but had not failed a TNF blocker. At baseline, and throughout the trial, approximately 39% of the subjects were receiving corticosteroids and 35% of the subjects were receiving immunomodulators (AZA, 6-MP, MTX). The median baseline CDAI score was 286 in the ustekinumab and 290 in the placebo group.

In these induction trials, a greater proportion of subjects treated with ustekinumab (at the recommended dose of approximately 6 mg/kg dose) achieved clinical response at Week 6 and clinical remission at Week 8 compared to placebo (see Table 12 for clinical response and remission rates). Clinical response and remission were significant as early as Week 3 in ustekinumab-treated subjects and continued to improve through Week 8.

Table 12: Induction of Clinical Response and Remission in CD-1 [Patient population consisted of subjects who failed or were intolerant to TNF blocker therapy] and CD-2 [Patient population consisted of subjects who failed or were intolerant to corticosteroids or immunomodulators (e.g., 6-MP, AZA, MTX) and previously received but not failed a TNF blocker or were never treated with a TNF blocker.]
 | CD-1 n = 741 |  |  | CD-2 n = 627
 | Placebo N = 247 | Ustekinumab [Infusion dose of ustekinumab using the weight-based dosage regimen specified in Table 3.] N = 249 | Treatment difference and 95% CI | Placebo N = 209 | Ustekinumab N = 209 | Treatment difference and 95% CI
Clinical Response (100 point), Week 6 | 53 (21%) | 84 (34%) [0.001≤ p < 0.01] | 12% (4%, 20%) | 60 (29%) | 116 (56%) [p < 0.001] | 27% (18%, 36%)
Clinical Remission, Week 8 | 18 (7%) | 52 (21%) | 14% (8%, 20%) | 41 (20%) | 84 (40%) | 21% (12%, 29%)
Clinical Response (100 point), Week 8 | 50 (20%) | 94 (38%) | 18% (10%, 25%) | 67 (32%) | 121 (58%) | 26% (17%, 35%)
70 Point Response, Week 6 | 75 (30%) | 109 (44%) | 13% (5%, 22%) | 81 (39%) | 135 (65%) | 26% (17%, 35%)
70 Point Response, Week 3 | 67 (27%) | 101 (41%) | 13% (5%, 22%) | 66 (32%) | 106 (51%) | 19% (10%, 28%)
Clinical remission is defined as CDAI score < 150; Clinical response is defined as reduction in CDAI score by at least 100 points or being in clinical remission: 70 point response is defined as reduction in CDAI score by at least 70 points

Trial CD-3

The maintenance trial (CD-3), evaluated 388 subjects who achieved clinical response (≥100 point reduction in CDAI score) at Week 8 with either induction dose of ustekinumab in trials CD-1 or CD-2. Subjects were randomized to receive a subcutaneous maintenance regimen of either 90 mg ustekinumab every 8 weeks or placebo for 44 weeks (see Table 13).

Table 13: Clinical Response and Remission in CD-3 (Week 44; 52 weeks from initiation of the induction dose)
 | Placebo [The placebo group consisted of subjects who were in response to ustekinumab and were randomized to receive placebo at the start of maintenance therapy.] N = 131 [Subjects who achieved clinical response to ustekinumab at the end of the induction trial.] | 90 mg Ustekinumab every 8 weeks N = 128 | Treatment difference and 95% CI
Clinical Remission | 47 (36%) | 68 (53%) [p < 0.01] | 17% (5%, 29%)
Clinical Response | 58 (44%) | 76 (59%) [0.01≤ p < 0.05] | 15% (3%, 27%)
Clinical Remission in subjects in remission at the start of maintenance therapy [Subjects in remission at the end of maintenance therapy who were in remission at the start of maintenance therapy. This does not account for any other time point during maintenance therapy.] | 36/79 (46%) | 52/78 (67%) | 21% (6%, 36%)
Clinical remission is defined as CDAI score < 150; Clinical response is defined as reduction in CDAI of at least 100 points or being in clinical remission

At Week 44, 47% of subjects who received ustekinumab were corticosteroid-free and in clinical remission, compared to 30% of subjects in the placebo group.

At Week 0 of trial CD-3, 34/56 (61%) ustekinumab-treated subjects who previously failed or were intolerant to TNF blocker therapies were in clinical remission and 23/56 (41%) of these subjects were in clinical remission at Week 44. In the placebo arm, 27/61 (44%) subjects were in clinical remission at Week 0 while 16/61 (26%) of these subjects were in remission at Week 44.

At Week 0 of trial CD-3, 46/72 (64%) ustekinumab-treated subjects who had previously failed immunomodulator therapy or corticosteroids (but not TNF blockers) were in clinical remission and 45/72 (63%) of these subjects were in clinical remission at Week 44. In the placebo arm, 50/70 (71%) of these subjects were in clinical remission at Week 0 while 31/70 (44%) were in remission at Week 44. In the subset of these subjects who were also naïve to TNF blockers, 34/52 (65%) of ustekinumab-treated subjects were in clinical remission at Week 44 as compared to 25/51 (49%) in the placebo arm.

Subjects who were not in clinical response 8 weeks after ustekinumab induction were not included in the primary efficacy analyses for trial CD-3; however, these subjects were eligible to receive a 90 mg subcutaneous injection of ustekinumab upon entry into trial CD-3. Of these subjects, 102/219 (47%) achieved clinical response eight weeks later and were followed for the duration of the trial.

14.5. Ulcerative Colitis

Ustekinumab was evaluated in two randomized, double-blind, placebo-controlled clinical trials [UC-1 and UC-2 (NCT02407236)] in adult subjects with moderately to severely active ulcerative colitis who had an inadequate response to or failed to tolerate a biologic (i.e., TNF blocker and/or vedolizumab), corticosteroids, and/or 6-MP or AZA therapy. The 8-week intravenous induction trial (UC-1) was followed by the 44-week subcutaneous randomized withdrawal maintenance trial (UC-2) for a total of 52 weeks of therapy.

Disease assessment was based on the Mayo score, which ranged from 0 to 12 and has four subscores that were each scored from 0 (normal) to 3 (most severe): stool frequency, rectal bleeding, findings on centrally-reviewed endoscopy, and physician global assessment. Moderately to severely active ulcerative colitis was defined at baseline (Week 0) as Mayo score of 6 to 12, including a Mayo endoscopy subscore ≥2. An endoscopy score of 2 was defined by marked erythema, absent vascular pattern, friability, erosions; and a score of 3 was defined by spontaneous bleeding, ulceration. At baseline, subjects had a median Mayo score of 9, with 84% of subjects having moderate disease (Mayo score 6-10) and 15% having severe disease (Mayo score 11-12).

Subjects in these trials may have received other concomitant therapies including aminosalicylates, immunomodulatory agents (AZA, 6-MP, or MTX), and oral corticosteroids (prednisone).

Trial UC-1

In UC-1, 961 subjects were randomized at Week 0 to a single intravenous administration of ustekinumab of approximately 6 mg/kg, 130 mg (a lower dose than recommended), or placebo. Subjects enrolled in UC-1 had to have failed therapy with corticosteroids, immunomodulators or at least one biologic. A total of 51% had failed at least one biologic and 17% had failed both a TNF blocker and an integrin receptor blocker. Of the total population, 46% had failed corticosteroids or immunomodulators but were biologic-naïve and an additional 3% had previously received but had not failed a biologic. At induction baseline and throughout the trial, approximately 52% subjects were receiving oral corticosteroids, 28% subjects were receiving immunomodulators (AZA, 6-MP, or MTX) and 69% subjects were receiving aminosalicylates.

The primary endpoint was clinical remission at Week 8. Clinical remission with a definition of: Mayo stool frequency subscore of 0 or 1, Mayo rectal bleeding subscore of 0 (no rectal bleeding), and Mayo endoscopy subscore of 0 or 1 (Mayo endoscopy subscore of 0 defined as normal or inactive disease and Mayo subscore of 1 defined as presence of erythema, decreased vascular pattern and no friability) is provided in Table 14.

The secondary endpoints were clinical response, endoscopic improvement, and histologic- endoscopic mucosal improvement. Clinical response with a definition of (≥ 2 points and ≥ 30% decrease in modified Mayo score, defined as 3-component Mayo score without the Physician's Global Assessment, with either a decrease from baseline in the rectal bleeding subscore ≥1 or a rectal bleeding subscore of 0 or 1), endoscopic improvement with a definition of Mayo endoscopy subscore of 0 or 1, and histologic-endoscopic mucosal improvement with a definition of combined endoscopic improvement and histologic improvement of the colon tissue [neutrophil infiltration in <5% of crypts, no crypt destruction, and no erosions, ulcerations, or granulation tissue]) are provided in Table 14.

In UC-1, a significantly greater proportion of subjects treated with ustekinumab (at the recommended dose of approximately 6 mg/kg dose) were in clinical remission and response and achieved endoscopic improvement and histologic-endoscopic mucosal improvement compared to placebo (see Table 14).

Table 14: Proportion of Subjects Meeting Efficacy Endpoints at Week 8 in UC-1
Endpoint | Placebo N = 319 |  | Ustekinumab [Infusion dose of ustekinumab using the weight-based dosage regimen specified in Table 3.] N = 322 |  | Treatment difference and 97.5% CI [Adjusted treatment difference (97.5% CI)]
Endpoint | N | % | N | % | Treatment difference and 97.5% CI [Adjusted treatment difference (97.5% CI)]
Clinical Remission [Clinical remission was defined as Mayo stool frequency subscore of 0 or 1, Mayo rectal bleeding subscore of 0, and Mayo endoscopy subscore of 0 or 1 (modified so that 1 does not include friability).] | 22 | 7% | 62 | 19% | 12% (7%, 18%) [p < 0.001]
Bio-naive [An additional 7 subjects on placebo and 9 subjects on ustekinumab (6 mg/kg) had been exposed to, but had not failed, biologics.] | 14/151 | 9% | 36/147 | 24%
Prior biologic failure | 7/161 | 4% | 24/166 | 14%
Endoscopic Improvement [Endoscopic improvement was defined as Mayo endoscopy subscore of 0 or 1 (modified so that 1 does not include friability).] | 40 | 13% | 80 | 25% | 12% (6%, 19%)
Bio-naive | 28/151 | 19% | 43/147 | 29%
Prior biologic failure | 11/161 | 7% | 34/166 | 20%
Clinical Response [Clinical response was defined as a decrease from baseline in the modified Mayo score by ≥30% and ≥2 points, with either a decrease from baseline in the rectal bleeding subscore ≥1 or a rectal bleeding subscore of 0 or 1.] | 99 | 31% | 186 | 58% | 27% (18%, 35%)
Bio-naive | 55/151 | 36% | 94/147 | 64%
Prior biologic failure | 42/161 | 26% | 86/166 | 52%
Histologic-Endoscopic Mucosal Improvement [Histologic-endoscopic mucosal improvement was defined as combined endoscopic improvement (Mayo endoscopy subscore of 0 or 1) and histologic improvement of the colon tissue (neutrophil infiltration in <5% of crypts, no crypt destruction, and no erosions, ulcerations, or granulation tissue).] | 26 | 8% | 54 | 17% | 9% (3%, 14%)
Bio-naive | 19/151 | 13% | 30/147 | 20%
Prior biologic failure | 6/161 | 4% | 21/166 | 13%

The relationship of histologic-endoscopic mucosal improvement, as defined in UC-1, at Week 8 to disease progression and long-term outcomes was not evaluated during UC-1.

Rectal Bleeding and Stool Frequency Subscores

Decreases in rectal bleeding and stool frequency subscores were observed as early as Week 2 in ustekinumab-treated subjects.

Trial UC-2

The maintenance trial (UC-2) evaluated 523 subjects who achieved clinical response 8 weeks following the intravenous administration of either induction dose of ustekinumab in UC-1. These subjects were randomized to receive a subcutaneous maintenance regimen of either 90 mg ustekinumab every 8 weeks, or every 12 weeks (a lower dose than recommended), or placebo for 44 weeks.

The primary endpoint was the proportion of subjects in clinical remission at Week 44. The secondary endpoints included the proportion of subjects maintaining clinical response at Week 44, the proportion of subjects with endoscopic improvement at Week 44, the proportion of subjects with corticosteroid-free clinical remission at Week 44, and the proportion of subjects maintaining clinical remission at Week 44 among subjects who achieved clinical remission 8 weeks after induction.

Results of the primary and secondary endpoints at Week 44 in subjects treated with ustekinumab at the recommended dosage (90 mg every 8 weeks) compared to the placebo are shown in Table 15.

Table 15: Efficacy Endpoints of Maintenance at Week 44 in UC-2 (52 Weeks from Initiation of the Induction Dose)
Endpoint | Placebo [The placebo group consisted of subjects who were in response to ustekinumab and were randomized to receive placebo at the start of maintenance therapy.] N = 175 [Clinical response was defined as a decrease from baseline in the modified Mayo score by ≥30% and ≥2 points, with either a decrease from baseline in the rectal bleeding subscore ≥1 or a rectal bleeding subscore of 0 or 1.] |  | 90 mg Ustekinumab every 8 weeks N = 176 |  | Treatment difference and 95% CI
Endpoint | N | % | N | % | Treatment difference and 95% CI
Clinical Remission [Clinical remission was defined as Mayo stool frequency subscore of 0 or 1, Mayo rectal bleeding subscore of 0, and Mayo endoscopy subscore of 0 or 1 (modified so that 1 does not include friability).] | 46 | 26% | 79 | 45% | 19% (9%, 28%) [p =<0.001]
Bio-naïve [An additional 3 subjects on placebo and 6 subjects on ustekinumab had been exposed to, but had not failed, biologics.] | 30/84 | 36% | 39/79 | 49%
Prior biologic failure | 16/88 | 18% | 37/91 | 41%
Maintenance of Clinical Response at Week 44 | 84 | 48% | 130 | 74% | 26% (16%, 36%)
Bio-naïve | 49/84 | 58% | 62/79 | 78%
Prior biologic failure | 35/88 | 40% | 64/91 | 70%
Endoscopic Improvement [Endoscopic improvement was defined as Mayo endoscopy subscore of 0 or 1 (modified so that 1 does not include friability).] | 47 | 27% | 83 | 47% | 20% (11%, 30%)
Bio-naïve | 29/84 | 35% | 42/79 | 53%
Prior biologic failure | 18/88 | 20% | 38/91 | 42%
Corticosteroid-free Clinical Remission [Corticosteroid-free clinical remission was defined as subjects in clinical remission and not receiving corticosteroids at Week 44.] | 45 | 26% | 76 | 43% | 17% (8%, 27%)
Bio-naïve | 30/84 | 36% | 38/79 | 48%
Prior biologic failure | 15/88 | 17% | 35/91 | 38%
Maintenance of Clinical Remission at Week 44 in subjects who achieved clinical remission 8 weeks after induction | 18/50 | 36% | 27/41 | 66% | 31% (12%, 50%) [p=0.004]
Bio-naïve | 12/27 | 44% | 14/20 | 70%
Prior biologic failure | 6/23 | 26% | 12/18 | 67%

Other Endpoints

Week 16 Responders to Ustekinumab Induction

Subjects who were not in clinical response 8 weeks after induction with ustekinumab in UC-1 were not included in the primary efficacy analyses for trial UC-2; however, these subjects were eligible to receive a 90 mg subcutaneous injection of ustekinumab at Week 8. Of these subjects, 55/101 (54%) achieved clinical response eight weeks later (Week 16) and received ustekinumab 90 mg subcutaneously every 8 weeks during the UC-2 trial. At Week 44, there were 97/157 (62%) subjects who maintained clinical response and there were 51/157 (32%) who achieved clinical remission.

Histologic-Endoscopic Mucosal Improvement at Week 44

The proportion of subjects achieving histologic-endoscopic mucosal improvement during maintenance treatment in UC-2 was 75/172 (44%) among subjects on ustekinumab and 40/172 (23%) in subjects on placebo at Week 44. The relationship of histologic-endoscopic mucosal improvement, as defined in UC-2, at Week 44 to progression of disease or long-term outcomes was not evaluated in UC-2.

Endoscopic Normalization

Normalization of endoscopic appearance of the mucosa was defined as a Mayo endoscopic subscore of 0. At Week 8 in UC-1, endoscopic normalization was achieved in 25/322 (8%) of subjects treated with ustekinumab and 12/319 (4%) of subjects in the placebo group. At Week 44 of UC-2, endoscopic normalization was achieved in 51/176 (29%) of subjects treated with ustekinumab and in 32/175 (18%) of subjects in placebo group.

15. REFERENCES

^1 Surveillance, Epidemiology, and End Results (SEER) Program (www.seer.cancer.gov) SEER*Stat Database: Incidence - SEER 6.6.2 Regs Research Data, Nov 2009 Sub (1973- 2007) - Linked To County Attributes - Total U.S., 1969-2007 Counties, National Cancer Institute, DCCPS, Surveillance Research Program, Surveillance Systems Branch, released April 2010, based on the November 2009 submission.

16. HOW SUPPLIED/STORAGE AND HANDLING

STEQEYMA (ustekinumab-stba) injection is a sterile, preservative-free, colorless to pale yellow solution and may contain a few small translucent or white particles. It is supplied as individually packaged, single-dose prefilled syringes or single-dose vials.

For Subcutaneous Use

Prefilled Syringes

- 45 mg/0.5 mL (NDC 72606-027-01)
- 90 mg/mL (NDC 72606-028-01)

Each prefilled syringe is equipped with a 27-gauge fixed ½ inch needle, a needle safety guard, and a needle cover.

For Intravenous Infusion

Single-dose Vial

- 130 mg/26 mL (5 mg/mL) (NDC 72606-029-01)

Storage and Stability

Store STEQEYMA vials and prefilled syringes refrigerated between 2ºC to 8ºC (36ºF to 46ºF). Store STEQEYMA vials upright. Keep the product in the original carton to protect from light until the time of use. Do not freeze. Do not shake.

If needed, individual vials and prefilled syringes may be stored at room temperature up to 30°C (86°F) for a maximum single period of up to 15 days in the original carton to protect from light. Record the date when the vial or the prefilled syringe is first removed from the refrigerator on the carton in the space provided. Once a vial or a syringe has been stored at room temperature, do not return to the refrigerator. Discard the vial or syringe if not used within 15 days at room temperature storage. Do not use STEQEYMA after the expiration date on the carton or on the vial or the prefilled syringe.

17. PATIENT COUNSELING INFORMATION

Advise the patient and/or caregiver to read the FDA-approved patient labeling (Medication Guide and Instructions for Use).

Infections

Inform patients that STEQEYMA may lower the ability of their immune system to fight infections and to contact their healthcare provider immediately if they develop any signs or symptoms of infection [see Warnings and Precautions (5.1)].

Malignancies

Inform patients of the risk of developing malignancies while receiving STEQEYMA [see Warnings and Precautions (5.4)].

Hypersensitivity Reactions

- Advise patients to seek immediate medical attention if they experience any signs or symptoms of serious hypersensitivity reactions and discontinue STEQEYMA [see Warnings and Precautions (5.5)].

Posterior Reversible Encephalopathy Syndrome (PRES)

Inform patients to immediately contact their healthcare provider if they experience signs and symptoms of PRES (which may include headache, seizures, confusion, or visual disturbances) [see Warnings and Precautions (5.6)].

Immunizations

Inform patients that STEQEYMA can interfere with the usual response to immunizations and that they should avoid live vaccines [see Warnings and Precautions (5.7)].

Administration

Instruct patients to follow sharps disposal recommendations, as described in the Instructions for Use.

STEQEYMA®
(ustekinumab-stba)

Manufactured by:
CELLTRION, Inc.
23, Academy-ro, Yeonsu-gu,
Incheon, 22014, Republic of Korea
US License No.: 1996

Distributed by:
CELLTRION USA, Inc.
One Evertrust Plaza Suite 1207,
Jersey City, New Jersey,
07302, USA

MEDICATION GUIDE
STEQEYMA (ste-qey-ma)
(ustekinumab-stba)
injection, for subcutaneous or intravenous use

What is the most important information I should know about STEQEYMA?
STEQEYMA is a medicine that affects your immune system. STEQEYMA can increase your risk of having serious side effects, including:
Serious infections. STEQEYMA may lower the ability of your immune system to fight infections and may increase your risk of infections. Some people have serious infections while taking ustekinumab products, including tuberculosis (TB), and infections caused by bacteria, fungi, or viruses. Some people have to be hospitalized for treatment of their infection.

- Your doctor should check you for TB before starting STEQEYMA.
- If your doctor feels that you are at risk for TB, you may be treated with medicine for TB before you begin treatment with STEQEYMA and during treatment with STEQEYMA.
- Your doctor should watch you closely for signs and symptoms of TB while you are being treated with STEQEYMA. You should not start taking STEQEYMA if you have any kind of infection unless your doctor says it is okay.

Before starting STEQEYMA, tell your doctor if you:

- think you have an infection or have symptoms of an infection such as:

- fever, sweat, or chills
- muscle aches
- cough
- shortness of breath
- blood in phlegm

- weight loss
- warm, red, or painful skin or sores on your body
- diarrhea or stomach pain
- burning when you urinate or urinate more often than normal
- feel very tired

- are being treated for an infection or have any open cuts.
- get a lot of infections or have infections that keep coming back.
- have TB, or have been in close contact with someone with TB.

After starting STEQEYMA, call your doctor right away if you have any symptoms of an infection (see above). These may be signs of infections such as chest infections, or skin infections or shingles that could have serious complications. STEQEYMA can make you more likely to get infections or make an infection that you have worse. People who have a genetic problem where the body does not make any of the proteins interleukin 12 (IL-12) and interleukin 23 (IL-23) are at a higher risk for certain serious infections. These infections can spread throughout the body and cause death. People who take STEQEYMA may also be more likely to get these infections.
Cancers. STEQEYMA may decrease the activity of your immune system and increase your risk for certain types of cancers. Tell your doctor if you have ever had any type of cancer. Some people who are receiving ustekinumab products and have risk factors for skin cancer have developed certain types of skin cancers. During your treatment with STEQEYMA, tell your doctor if you develop any new skin growths.
Posterior Reversible Encephalopathy Syndrome (PRES). PRES is a rare condition that affects the brain and can cause death. The cause of PRES is not known. If PRES is found early and treated, most people recover. Tell your doctor right away if you have any new or worsening medical problems including:

- headache
- seizures

- confusion
- vision problems

What is STEQEYMA?
STEQEYMA is a prescription medicine used to treat:

- adults and children 6 years and older with moderate or severe psoriasis who may benefit from taking injections or pills (systemic therapy) or phototherapy (treatment using ultraviolet light alone or with pills).
- adults and children 6 years and older with active psoriatic arthritis.
- adults 18 years and older with moderately to severely active Crohn's disease.
- adults 18 years and older with moderately to severely active ulcerative colitis.

It is not known if STEQEYMA is safe and effective in children less than 6 years of age.
Do not take STEQEYMA if you are allergic to ustekinumab products or any of the ingredients in STEQEYMA. See the end of this Medication Guide for a complete list of ingredients in STEQEYMA.

Before you receive STEQEYMA, tell your doctor about all of your medical conditions, including if you:

- have any of the conditions or symptoms listed in the section "What is the most important information I should know about STEQEYMA?"
- ever had an allergic reaction to ustekinumab products. Ask your doctor if you are not sure.
- have recently received or are scheduled to receive an immunization (vaccine). People who take STEQEYMA should not receive live vaccines. Tell your doctor if anyone in your house needs a live vaccine. The viruses used in some types of live vaccines can spread to people with a weakened immune system, and can cause serious problems. You should not receive the BCG vaccine during the one year before receiving STEQEYMA or one year after you stop receiving STEQEYMA.
- have any new or changing lesions within psoriasis areas or on normal skin.
- are receiving or have received allergy shots, especially for serious allergic reactions. Allergy shots may not work as well for you during treatment with STEQEYMA. STEQEYMA may also increase your risk of having an allergic reaction to an allergy shot.
- receive or have received phototherapy for your psoriasis.
- are pregnant or plan to become pregnant. It is not known if STEQEYMA can harm your unborn baby. You and your doctor should decide if you will receive STEQEYMA. See "What should I avoid while using STEQEYMA?"
- received STEQEYMA while you were pregnant. It is important that you tell your baby's healthcare provider before any vaccinations are given to your baby.
- are breastfeeding or plan to breastfeed. STEQEYMA can pass into your breast milk.
- Talk to your doctor about the best way to feed your baby if you receive STEQEYMA.

Tell your doctor about all the medicines you take, including prescription and over-the-counter medicines, vitamins, and herbal supplements.
Know the medicines you take. Keep a list of them to show your doctor and pharmacist when you get a new medicine.

How should I use STEQEYMA?

- Use STEQEYMA exactly as your doctor tells you to.
- Adults with Crohn's disease and ulcerative colitis will receive the first dose of STEQEYMA through a vein in the arm (intravenous infusion) in a healthcare facility by a healthcare provider. It takes at least 1 hour to receive the full dose of medicine. You will then receive STEQEYMA as an injection under the skin (subcutaneous injection) 8 weeks after the first dose of STEQEYMA, as described below.
- Adults with psoriasis or psoriatic arthritis, and children 6 years and older with psoriasis or psoriatic arthritis will receive STEQEYMA as an injection under the skin (subcutaneous injection) as described below.
- Injecting STEQEYMA under your skin
  - STEQEYMA is intended for use under the guidance and supervision of your doctor. In children 6 years and older, it is recommended that STEQEYMA be administered by a healthcare provider. If your doctor decides that you or a caregiver may give your injections of STEQEYMA at home, you should receive training on the right way to prepare and inject STEQEYMA. Your doctor will determine the right dose of STEQEYMA for you, the amount for each injection, and how often you should receive it. Do not try to inject STEQEYMA yourself until you or your caregiver have been shown how to inject STEQEYMA by your doctor or nurse.
  - Inject STEQEYMA under the skin (subcutaneous injection) in your upper arms, buttocks, upper legs (thighs) or stomach area (abdomen).
  - Do not give an injection in an area of the skin that is tender, bruised, red or hard.
  - Use a different injection site each time you use STEQEYMA.
  - If you inject more STEQEYMA than prescribed, call your doctor right away.
  - Be sure to keep all of your scheduled follow-up appointments.

Read the detailed Instructions for Use at the end of this Medication Guide for instructions about how to prepare and inject a dose of STEQEYMA, and how to properly throw away (dispose of) used needles and syringes. The syringe, needle and vial must never be re-used. After the rubber stopper is punctured,
STEQEYMA can become contaminated by harmful bacteria which could cause an infection if re-used. Therefore, throw away any unused portion of STEQEYMA.

What should I avoid while using STEQEYMA?
You should not receive a live vaccine while taking STEQEYMA. See "Before you receive STEQEYMA, tell your doctor about all of your medical conditions, including if you:"

What are the possible side effects of STEQEYMA?
STEQEYMA may cause serious side effects, including:

- See "What is the most important information I should know about STEQEYMA?"
- Serious allergic reactions. Serious allergic reactions can occur with STEQEYMA. Stop using STEQEYMA and get medical help right away if you have any of the following symptoms of a serious allergic reaction:

- feeling faint
- swelling of your face, eyelids, tongue, or throat

- chest tightness
- skin rash

- Lung inflammation. Cases of lung inflammation have happened in some people who receive ustekinumab products, and may be serious. These lung problems may need to be treated in a hospital. Tell your doctor right away if you develop shortness of breath or a cough that doesn't go away during treatment with STEQEYMA.

Common side effects of STEQEYMA include:

- nasal congestion, sore throat, and runny nose
- upper respiratory infections
- fever
- headache
- tiredness
- itching
- nausea and vomiting

- redness at the injection site
- vaginal yeast infections
- urinary tract infections
- sinus infection
- bronchitis
- diarrhea
- stomach pain

These are not all of the possible side effects of STEQEYMA. Call your doctor for medical advice about side effects. You may report side effects to FDA at 1-800-FDA-1088.
You may also report side effects to CELLTRION USA, Inc. at 1-800-560-9414.

How should I store STEQEYMA?

- Store STEQEYMA vials and prefilled syringes in a refrigerator between 36°F to 46°F (2°C to 8°C).
- Store STEQEYMA vials standing up straight.
- Store STEQEYMA in the original carton to protect it from light until time to use it.
- Do not freeze STEQEYMA.
- Do not shake STEQEYMA.

If needed, individual STEQEYMA vials and prefilled syringes may also be stored at room temperature up to 86ºF (30°C) for a maximum single period of up to 15 days in the original carton to protect from light. Record the date when the vial or the prefilled syringe is first removed from the refrigerator on the carton in the space provided. Once a vial or a syringe has been stored at room temperature, it should not be returned to the refrigerator. Discard the vial or syringe if not used within 15 days at room temperature storage. Do not use STEQEYMA after the expiration date on the carton or on the vial or the prefilled syringe.
Keep STEQEYMA and all medicines out of the reach of children.

General information about the safe and effective use of STEQEYMA.
Medicines are sometimes prescribed for purposes other than those listed in a Medication Guide. Do not use STEQEYMA for a condition for which it was not prescribed. Do not give STEQEYMA to other people, even if they have the same symptoms that you have. It may harm them. You can ask your doctor or pharmacist for information about STEQEYMA that was written for health professionals.

What are the ingredients in STEQEYMA?
Active ingredient: ustekinumab-stba
Inactive ingredients: Single-dose prefilled syringe for subcutaneous use contains histidine, L-histidine monohydrochloride monohydrate, polysorbate 80, sucrose, and Water for Injection. Single-dose vial for intravenous infusion contains edetate disodium, histidine, L-histidine monohydrochloride monohydrate, methionine, polysorbate 80, sucrose, and Water for Injection.
Manufactured by: CELLTRION, Inc. 23, Academy-ro, Yeonsu-gu, Incheon, 22014, Republic of Korea, US License No. 1996
Distributed by: CELLTRION USA, Inc. One Evertrust Plaza Suite 1207, Jersey City, New Jersey, 07302, USA
For more information go to www.steqeyma.com or call 1-888-804-3433.

This Medication Guide has been approved by the U.S. Food and Drug Administration.

Approved: 12/2024

INSTRUCTIONS FOR USE STEQEYMA (ste-qey-ma) (ustekinumab-stba) injection, for subcutaneous use

Instructions for injecting STEQEYMA using a prefilled syringe.

This Instructions for Use contains information on how to inject STEQEYMA. Read and follow this Instructions for Use before you start using STEQEYMA. Your doctor or nurse should show you how to prepare and give your injection of STEQEYMA the right way.

If you cannot give yourself the injection:

- ask your doctor or nurse to help you, or
- ask someone who has been trained by a doctor or nurse to give your injections.

Do not try to inject STEQEYMA yourself until you have been shown how to inject STEQEYMA by your doctor, nurse or health professional.

STEQEYMA prefilled syringes are available in 2 dose strengths (see Figure A). These instructions can be used for both dose strengths.

Figure A

Figure A

Important Information

- Before you start, check the carton to make sure that it is the right dose. You will have either 45 mg or 90 mg as prescribed by your doctor.
  - If your dose is 45 mg, you will receive one 45 mg prefilled syringe.
  - If your dose is 90 mg, you will receive either one 90 mg prefilled syringe or two 45 mg prefilled syringes. If you receive two 45 mg prefilled syringes for a 90 mg dose, you will need to give yourself two injections, one right after the other.
- Children 12 years of age and older with psoriasis who weigh 132 pounds or more may use a prefilled syringe.
- Do not use the prefilled syringe if the liquid is discolored, cloudy, or has large particles. Get a new prefilled syringe.
- Do not shake the prefilled syringe at any time. Shaking your prefilled syringe may damage your STEQEYMA medicine. If your prefilled syringe has been shaken, do not use it. Get a new prefilled syringe.
- To reduce the risk of accidental needle sticks, each prefilled syringe has a needle guard that is automatically activated to cover the needle after you have given your injection. Do not pull back on the plunger rod at any time.

Storing STEQEYMA

- Store the STEQEYMA prefilled syringe in a refrigerator between 36°F to 46°F (2°C to 8ºC).
- Store STEQEYMA in the original carton to protect it from light until time to use it.
- Do not freeze STEQEYMA.
- Do not shake STEQEYMA.
- If needed, individual STEQEYMA prefilled syringes may be stored at room temperature up to 86℉ (30℃) for a maximum single period of up to 15 days in the original carton to protect from light. Record the date when the prefilled syringe is first removed from the refrigerator on the carton in the space provided. When a syringe has been stored at room temperature, it should not be returned to the refrigerator. Throw away (discard) the syringe if not used within 15 days at room temperature storage. Do not use STEQEYMA after the expiration date on the carton or the prefilled syringe.
- Keep STEQEYMA and all medicines out of the reach of children.

Parts of the Prefilled Syringe (see Figure B)

Figure B

Figure B

Preparing to Inject STEQEYMA

Figure C

1.Gather the supplies for the injection1.a.Prepare a clean, ﬂat surface, such as a table or counter top, in a well-lit area.1.b. Take the carton(s) containing the prefilled syringe(s) needed to administer your prescribed dose out of the refrigerator. Each STEQEYMA carton contains 1 prefilled syringe.
Note: Depending on the dose prescribed to you by your healthcare provider you may need to prepare 1 or more prefilled syringes and inject the contents of them all.1.c. Make sure you have the following supplies (see Figure C)- Carton containing preﬁlled syringe
Not included in the carton:- Cotton ball or gauze- Adhesive bandage- FDA-cleared sharps disposal container- Alcohol swab

Figure D

2.Check the expiration date on the carton (see Figure D).

- Do not use it if the expiration date has passed. If the expiration date has passed, safely throw away (dispose of) the carton in an FDA-cleared sharps disposal container (see step 13. Throw away (dispose of) STEQEYMA).

Figure E

3.Wait 30 minutes.3.a. Open the carton. Gripping from the syringe body, lift the prefilled syringe from the carton.3.b. Leave the prefilled syringe outside of the carton at room temperature 68°F to 77°F (20°C to 25°C) for 30 minutes to allow it to warm up (see Figure E).

- Do not warm the prefilled syringe using heat sources such as hot water or a microwave.
- If the prefilled syringe does not reach room temperature, this could cause the injection to feel uncomfortable and make it hard to push the plunger.

Figure F

4.Wash your hands.4.a. Wash your hands with soap and water and dry them thoroughly (see Figure F).

Figure G

5.Inspect the prefilled syringe.5.a. Look at the prefilled syringe and make sure you have the correct medicine (STEQEYMA) and dosage.5.b. Look at the prefilled syringe and make sure it is not cracked or damaged.5.c. Check the expiration date on the label of the prefilled syringe (see Figure G).

- Do not use if the expiration date has passed.

Figure H

6.Inspect the medicine.6.a. Look at the medicine and make sure that the liquid is clear to slightly opalescent and colorless to pale yellow. (see Figure H).

- Do not use the prefilled syringe if the liquid is discolored, cloudy, or has large particles. Get a new prefilled syringe.
- You may see air bubbles in the liquid. This is normal.

Figure I

7.Choose an injection site (see Figure I).7.a. Choose an injection site around your stomach area (abdomen), buttocks, upper legs (thighs). If a caregiver is giving you the injection, the outer area of the upper arms may also be used (see Figure I).

- Use a different injection site for each injection.
- Do not give an injection in an area of the skin that is tender, bruised, red or hard.

Figure J

8.Clean the injection site.8.a. Clean the skin with an alcohol swab where you plan to give your injection (see Figure J).

- Do not touch this area again before giving the injection. Let your skin dry before injecting.
- Do not fan or blow on the clean area.

Injecting STEQEYMA

Figure K

9.Remove the cap.9.a. Remove the needle cap when you are ready to inject your STEQEYMA by holding the body of the prefilled syringe in one hand between the thumb and index fingers (see Figure K).

- Do not hold the plunger while removing the cap.
- You may see a drop of liquid at the tip of the needle. This is normal.

9.b. Throw away (dispose of) the cap right away in an FDA-cleared sharps disposal container (see step 13. Throw away (dispose of) STEQEYMA).

- Do not re-cap the prefilled syringe.
- Do not touch the needle. Doing so may result in a needle stick injury.
- Do not use the prefilled syringe if it has been dropped without the needle cover in place. Call your doctor, nurse or health professional for further instructions.

Figure L

10.Insert the prefilled syringe into the injection site.10.a. Hold the body of the prefilled syringe in one hand between the thumb and index fingers (see Figure L).10.b. Gently pinch a fold of skin at the injection site with one hand.
Note: Pinching the skin is important to make sure that you inject under the skin (into the fatty area) but not any deeper (into muscle).10.c. With a quick and dart-like motion, insert the needle completely into the fold of skin at a 45-degree angle (see Figure L).

- Do not pull back on the plunger rod at any time.

Figure M

11.Give the injection.11.a. After the needle is inserted, release the pinch.11.b. Inject all of the liquid by using your thumb to push the plunger all the way down (see Figure M).

- If the plunger is not fully pressed, the needle guard will not extend to cover the needle when it is removed.

Figure N

12.Remove the prefilled syringe from the injection site.12.a. After the prefilled syringe is empty, slowly lift your thumb from the plunger rod until the needle is completely covered by the needle guard (see Figure N).

- If the needle is not covered, proceed carefully to throw away (dispose of) the syringe (see step 13. Throw away (dispose of) STEQEYMA).
- Some bleeding may occur. This is normal (see step 14. Care for the injection site).
- Do not rub the injection site.

If your dose is 90 mg, you will receive either one 90 mg prefilled syringe or two 45 mg prefilled syringes. If you receive two 45 mg prefilled syringes for a 90 mg dose, you will need to give yourself a second injection right after the first. Repeat Steps 1 to 12 for the second injection using a new syringe. Choose a different site for the second injection.

After the Injection

Figure O

13. Throw away (dispose of) STEQEYMA.

13.a. Put the used prefilled syringe in an FDA-cleared sharps disposal container right away after use (see Figure O).

- STEQEYMA prefilled syringe is a single-dose syringe and should not be used again.
- Do not throw away (dispose of) the prefilled syringe in your household trash.
- If you do not have an FDA-cleared sharps disposal container, you may use a household container that is:- made of a heavy-duty plastic,- can be closed with a tight-fitting, puncture-resistant lid, without sharps being able to come out,- upright and stable during use,- leak-resistant, and- properly labeled to warn of hazardous waste inside the container.
- When your sharps disposal container is almost full, you will need to follow your community guidelines for the right way to dispose of it. There may be state or local laws about how you should throw away used needles and syringes. For more information about safe sharps disposal, and for specific information about sharps disposal in the state that you live in, go to the FDA's website at: http://www.fda.gov/safesharpsdisposal.
- Do not dispose of your used sharps disposal container in your household trash unless your community guidelines permit this.
- Do not recycle your used sharps disposal container.

14. Care for the injection site.
14.a. If some bleeding occurs, treat the injection site by gently pressing, not rubbing, a cotton ball or gauze to the site and apply an adhesive bandage if needed.

If you have any questions about using your STEQEYMA prefilled syringe, please call your healthcare provider or Company at 1-888-804-3433.

Manufactured by: CELLTRION, Inc. 23, Academy-ro, Yeonsu-gu, Incheon, 22014, Republic of Korea, US License No. 1996

Distributed by: CELLTRION USA, Inc. One Evertrust Plaza Suite 1207, Jersey City, New Jersey, 07302, USA

This Instructions for Use has been approved by the U.S. Food and Drug Administration.

Approved: 12/2024

PRINCIPAL DISPLAY PANEL - 45 mg/0.5 mL Syringe Carton

1 Single-dose Prefilled Syringe with Safety Guard
Discard unused portion

SteQeyma®
(ustekinumab-stba)
Injection

Rx only

1 prefilled syringe with safety guard
x 1

45 mg/0.5 mL

For subcutaneous use only

Attention: Dispense the enclosed

Medication Guide to each patient.

NDC 72606-027-01

CELLTRION USA
CELLTRION

PRINCIPAL DISPLAY PANEL - 90 mg/mL Syringe Carton

1 Single-dose Prefilled Syringe with Safety Guard
Discard unused portion

SteQeyma®
(ustekinumab-stba)
Injection

Rx only

1 prefilled syringe with safety guard
x 1

90 mg/mL

For subcutaneous use only

Attention: Dispense the enclosed

Medication Guide to each patient.

NDC 72606-028-01

CELLTRION USA
CELLTRION

PRINCIPAL DISPLAY PANEL - 130 mg/26 mL Vial Carton

NDC 72606-029-01
Rx only

SteQeyma®
(ustekinumab-stba)

Injection
130 mg/26 mL
(5 mg/mL)

For intravenous infusion only
Must be diluted
Single-Dose Vial
Discard Unused Portion

ATTENTION: Dispense
the enclosed Medication Guide
to each patient.

1 vial

CELLTRION USA
CELLTRION